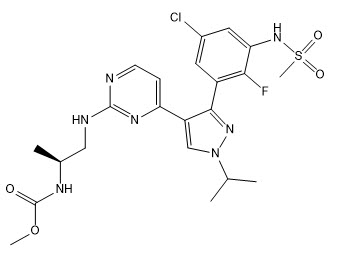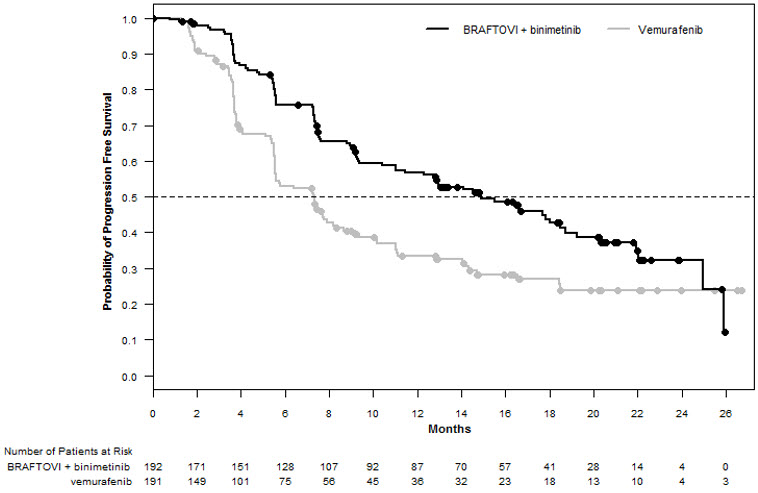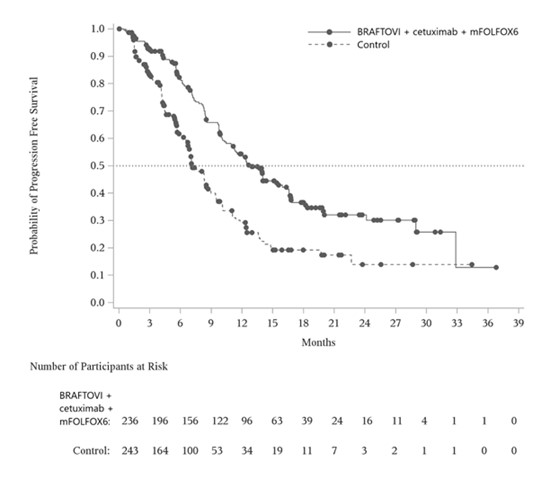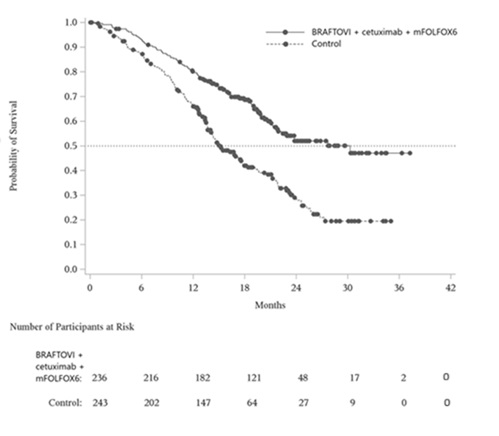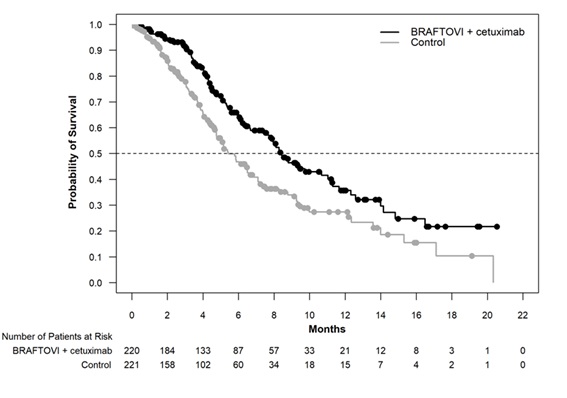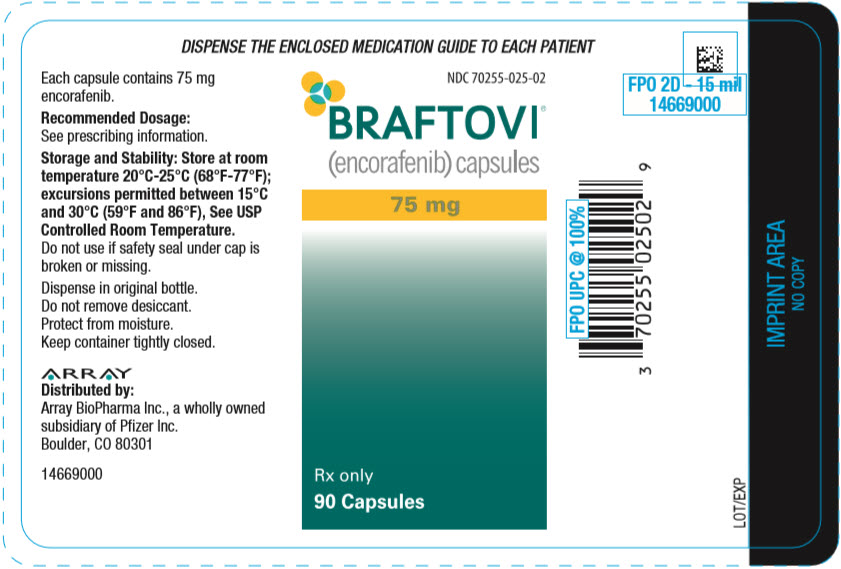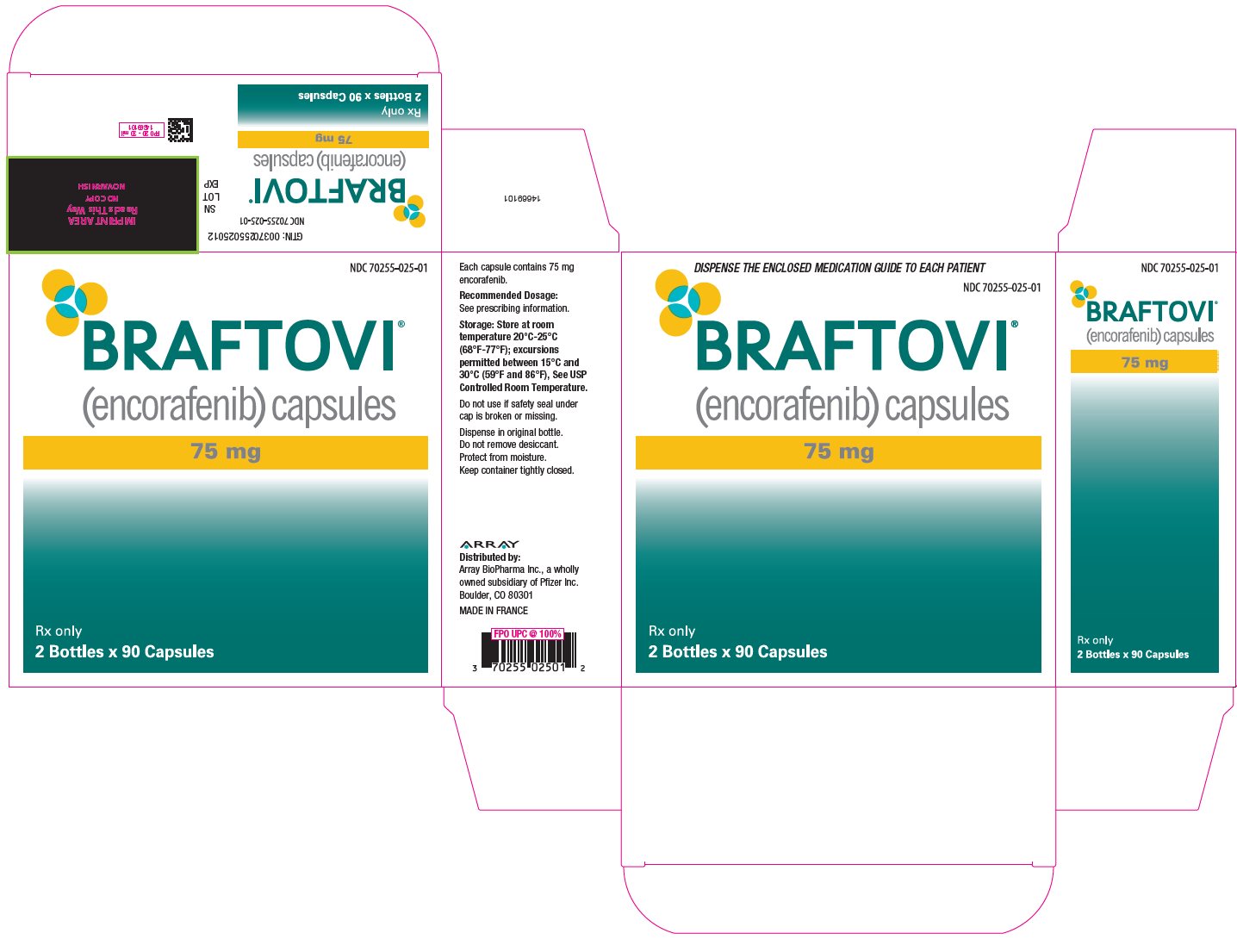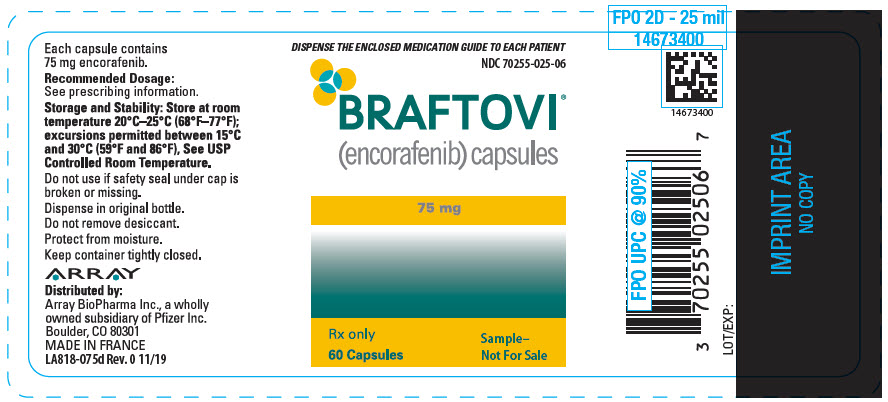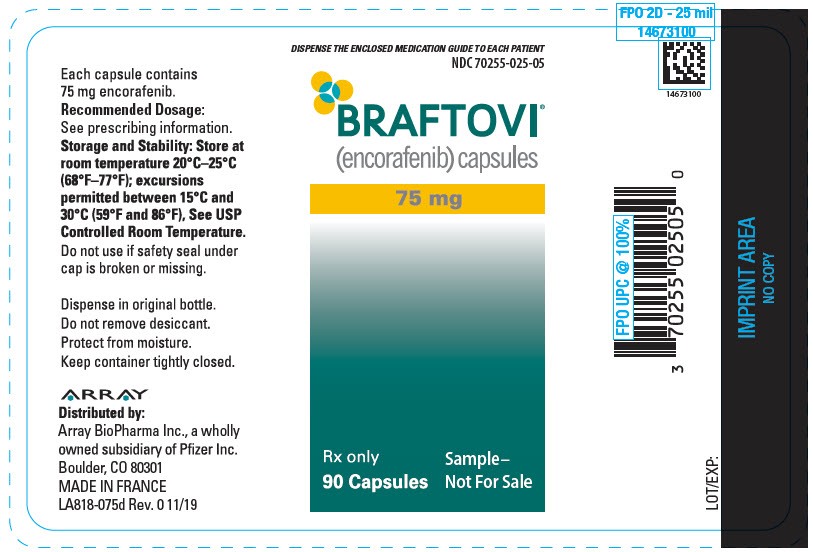 DRUG LABEL: BRAFTOVI
NDC: 70255-025 | Form: CAPSULE
Manufacturer: Array BioPharma Inc.
Category: prescription | Type: HUMAN PRESCRIPTION DRUG LABEL
Date: 20260226

ACTIVE INGREDIENTS: ENCORAFENIB 75 mg/1 1
INACTIVE INGREDIENTS: COPOVIDONE K25-31; POLOXAMER 188; MICROCRYSTALLINE CELLULOSE; SUCCINIC ACID; CROSPOVIDONE, UNSPECIFIED; SILICON DIOXIDE; MAGNESIUM STEARATE; GELATIN, UNSPECIFIED; TITANIUM DIOXIDE; FERRIC OXIDE RED; FERRIC OXIDE YELLOW; FERROSOFERRIC OXIDE; SHELLAC; PROPYLENE GLYCOL

HIGHLIGHTS OF PRESCRIBING INFORMATION

These highlights do not include all the information needed to use BRAFTOVI safely and effectively. See full prescribing information for BRAFTOVI.
BRAFTOVI® (encorafenib) capsules, for oral use
Initial U.S. Approval: 2018

RECENT MAJOR CHANGES

Indications and Usage (1.2) | 2/2026
Dosage and Administration (2.1, 2.3, 2.5) | 2/2026
Warnings and Precautions (5.1, 5.4, 5.5, 5.6, 5.7, 5.10) | 2/2026

1 INDICATIONS AND USAGE

BRAFTOVI is a kinase inhibitor indicated:

Melanoma

- in combination with binimetinib, for the treatment of patients with unresectable or metastatic melanoma with a BRAF V600E or V600K mutation, as detected by an FDA-authorized test. (1.1, 2.1)

Colorectal Cancer (CRC)

- in combination with cetuximab and fluorouracil-based chemotherapy, for the treatment of adult patients with metastatic colorectal cancer (mCRC) with a BRAF V600E mutation, as detected by an FDA‑authorized test. (1.2, 2.1)
- in combination with cetuximab, for the treatment of adult patients with mCRC with a BRAF V600E mutation, as detected by an FDA-authorized test, after prior therapy. (1.2, 2.1)

Non-Small Cell Lung Cancer (NSCLC)

- in combination with binimetinib, for the treatment of adult patients with metastatic non–small cell lung cancer (NSCLC) with a BRAF V600E mutation, as detected by an FDA-authorized test. (1.3, 2.1)

Limitations of Use

BRAFTOVI is not indicated for treatment of patients with wild-type BRAF melanoma, wild-type BRAF CRC, or wild-type BRAF NSCLC. (1.4, 5.2)

2 DOSAGE AND ADMINISTRATION

Melanoma

- Confirm the presence of BRAF V600E or V600K mutation in tumor specimens prior to the initiation of BRAFTOVI. (2.1)
- The recommended dose is 450 mg orally once daily in combination with binimetinib. (2.2)

CRC

- Confirm the presence of BRAF V600E mutation in plasma or tumor specimens prior to the initiation of BRAFTOVI. (2.1)
- The recommended dose is 300 mg orally once daily in combination with
  - biweekly cetuximab and mFOLFOX6 (fluorouracil, leucovorin and oxaliplatin) or cetuximab and FOLFIRI (fluorouracil, leucovorin and irinotecan) (2.3)
  - weekly cetuximab (2.3)

NSCLC

- Confirm the presence of BRAF V600E mutation in tumor or plasma specimens prior to initiating BRAFTOVI. (2.1)
- The recommended dose is 450 mg orally once daily in combination with binimetinib. (2.2)

Take BRAFTOVI with or without food. (2.4)

3 DOSAGE FORMS AND STRENGTHS

Capsules: 75 mg. (3)

4 CONTRAINDICATIONS

None. (4)

5 WARNINGS AND PRECAUTIONS

- New Primary Malignancies, cutaneous and noncutaneous: Can occur. Monitor for malignancies and perform dermatologic evaluations prior to, while on therapy, and following discontinuation of treatment. (5.1)
- Tumor Promotion in BRAF Wild-Type Tumors: Increased cell proliferation can occur with BRAF inhibitors. (5.2)
- Cardiomyopathy: Assess left ventricular ejection fraction (LVEF) before initiating treatment with BRAFTOVI and binimetinib, and after one month of treatment, then every 2 to 3 months thereafter. The safety of BRAFTOVI in combination with binimetinib has not been established in patients with LVEF below 50%. (5.3)
- Hepatotoxicity: Monitor liver function tests before and during treatment with BRAFTOVI and binimetinib and as clinically indicated. (5.4)
- Hemorrhage: Major hemorrhagic events can occur in patients receiving BRAFTOVI and binimetinib. (5.5)
- Uveitis: Perform ophthalmologic evaluation at regular intervals and for any visual disturbances. (5.6)
- QT Prolongation: Monitor electrolytes before and during treatment. Correct electrolyte abnormalities and control for cardiac risk factors for QT prolongation. Withhold BRAFTOVI for QTc of 500 ms or greater. (5.7)
- Embryo-Fetal Toxicity: Can cause fetal harm. Advise females with reproductive potential of potential risk to the fetus and to use effective nonhormonal method of contraception. (5.8, 8.1, 8.3)
- Risks Associated with BRAFTOVI as a Single Agent: If binimetinib is temporarily interrupted or permanently discontinued, reduce the dose of BRAFTOVI as recommended. (5.9)
- Risks Associated with Combination Treatment: BRAFTOVI is indicated for use as part of a regimen in combination with binimetinib or cetuximab. (5.10)

6 ADVERSE REACTIONS

- Melanoma: Most common adverse reactions (≥25%) for BRAFTOVI, in combination with binimetinib, are fatigue, nausea, vomiting, abdominal pain, and arthralgia. (6.1)
- CRC: Most common adverse reactions (≥25%) for BRAFTOVI, in combination with cetuximab and mFOLFOX6, are peripheral neuropathy, nausea, fatigue, diarrhea, decreased appetite, rash, vomiting, hemorrhage, abdominal pain, arthralgia, pyrexia, and constipation. (6.1)
- Most common adverse reactions (≥25%) for BRAFTOVI, in combination with cetuximab and FOLFIRI are nausea, diarrhea, fatigue, vomiting, alopecia, constipation, abdominal pain, decreased appetite, and rash. (6.1)
- Most common adverse reactions (≥25%) for BRAFTOVI, in combination with cetuximab, are fatigue, nausea, diarrhea, dermatitis acneiform, abdominal pain, decreased appetite, arthralgia, and rash. (6.1)
- NSCLC: Most common adverse reactions (≥25%) for BRAFTOVI, in combination with binimetinib, are fatigue, nausea, diarrhea, musculoskeletal pain, vomiting, abdominal pain, visual impairment, constipation, dyspnea, rash, and cough. (6.1)

To report SUSPECTED ADVERSE REACTIONS, contact Pfizer Inc. at 1-800-438-1985 or FDA at 1-800-FDA-1088 or www.fda.gov/medwatch.

7 DRUG INTERACTIONS

- Strong or moderate CYP3A4 inhibitors: Avoid coadministration. If unavoidable, reduce BRAFTOVI dosage. (2.6, 7.1)
- Strong CYP3A4 inducers: Avoid coadministration. (7.1)
- Sensitive CYP3A4 substrates: Avoid coadministration with CYP3A4 substrates (including hormonal contraceptives) for which a decrease in plasma concentration may lead to reduced efficacy of the substrate. (7.2)
- Transporters: Dose reductions of drugs that are substrates of OATP1B1, OATP1B3, or BCRP may be required when used concomitantly with BRAFTOVI. (7.2, 12.3)

8 USE IN SPECIFIC POPULATIONS

- Lactation: Advise not to breastfeed. (8.2)
- Males of Reproductive Potential: BRAFTOVI may impair fertility. (8.3)

FULL PRESCRIBING INFORMATION

1 INDICATIONS AND USAGE

1.1 BRAF V600E or V600K Mutation–Positive Unresectable or Metastatic Melanoma

BRAFTOVI is indicated, in combination with binimetinib, for the treatment of patients with unresectable or metastatic melanoma with a BRAF V600E or V600K mutation, as detected by an FDA-authorized test [see Dosage and Administration (2.1)].

1.2 BRAF V600E Mutation-Positive Metastatic Colorectal Cancer (mCRC)

- BRAFTOVI is indicated, in combination with cetuximab and fluorouracil-based chemotherapy, for the treatment of adult patients with metastatic colorectal cancer (mCRC) with a BRAF V600E mutation, as detected by an FDA-authorized test [see Dosage and Administration (2.1)].
- BRAFTOVI is indicated, in combination with cetuximab, for the treatment of adult patients with mCRC with a BRAF V600E mutation, as detected by an FDA-authorized test, after prior therapy [see Dosage and Administration (2.1)].

1.3 BRAF V600E Mutation-Positive Metastatic Non-Small Cell Lung Cancer (NSCLC)

BRAFTOVI is indicated, in combination with binimetinib, for the treatment of adult patients with metastatic non-small cell lung cancer (NSCLC) with a BRAF V600E mutation, as detected by an FDA-authorized test [see Dosage and Administration (2.1)].

1.4 Limitations of Use

BRAFTOVI is not indicated for treatment of patients with wild-type BRAF melanoma, wild-type BRAF CRC, or wild-type BRAF NSCLC [see Warnings and Precautions (5.2)].

2 DOSAGE AND ADMINISTRATION

2.1 Patient Selection

BRAF V600E or V600K Mutation-Positive Unresectable or Metastatic Melanoma

Confirm the presence of a BRAF V600E or V600K mutation in tumor specimens prior to initiating BRAFTOVI [see Warnings and Precautions (5.2), Clinical Studies (14.1)]. Information on FDA-authorized tests for the detection of BRAF V600E and V600K mutations in melanoma is available at: http://www.fda.gov/CompanionDiagnostics.

BRAF V600E Mutation-Positive Metastatic Colorectal Cancer (CRC)

Confirm the presence of a BRAF V600E mutation in plasma or tumor tissue prior to initiating BRAFTOVI [see Warnings and Precautions (5.2), Clinical Studies (14.2, 14.3)]. If no mutation is detected in a plasma specimen, test tumor tissue. Information on FDA-authorized tests for the detection of BRAF V600E mutations in CRC is available at: http://www.fda.gov/CompanionDiagnostics.

BRAF V600E Mutation-Positive Metastatic Non‑Small Cell Lung Cancer (NSCLC)

Confirm the presence of a BRAF V600E mutation in tumor or plasma specimens prior to initiating BRAFTOVI [see Warnings and Precautions (5.2), Clinical Studies (14.3)]. If no mutation is detected in a plasma specimen, test tumor tissue. Information on FDA-authorized tests for the detection of BRAF V600E mutations in NSCLC is available at: http://www.fda.gov/CompanionDiagnostics.

2.2 Recommended Dosage for BRAF V600E or V600K Mutation-Positive Unresectable or Metastatic Melanoma and for BRAF V600E Mutation-Positive Metastatic Non-Small Cell Lung Cancer (NSCLC)

The recommended dosage of BRAFTOVI is 450 mg (six 75 mg capsules) orally once daily in combination with binimetinib until disease progression or unacceptable toxicity. Refer to the binimetinib prescribing information for recommended binimetinib dosing information.

2.3 Recommended Dosage for BRAF V600E Mutation-Positive Metastatic Colorectal Cancer (CRC)

The recommended dosage of BRAFTOVI is 300 mg (four 75 mg capsules) orally once daily until disease progression or unacceptable toxicity in combination with:

- biweekly cetuximab and mFOLFOX6 (fluorouracil, leucovorin and oxaliplatin) or biweekly cetuximab and FOLFIRI (fluorouracil, leucovorin and irinotecan) [see Clinical Studies (14.2)]
- weekly cetuximab [see Clinical Studies (14.2)].

2.4 Administration

BRAFTOVI may be taken with or without food [see Clinical Pharmacology (12.3)]. Do not take a missed dose of BRAFTOVI within 12 hours of the next dose of BRAFTOVI.

Do not take an additional dose if vomiting occurs after BRAFTOVI administration but continue with the next scheduled dose.

2.5 Dosage Modifications for Adverse Reactions

BRAF V600E or V600K Mutation-Positive Unresectable or Metastatic Melanoma or BRAF V600E Mutation-Positive Metastatic NSCLC

If binimetinib is withheld, reduce BRAFTOVI to a maximum dose of 300 mg (four 75 mg capsules) once daily until binimetinib is resumed [see Warnings and Precautions (5.9)].

Dose reductions for adverse reactions associated with BRAFTOVI are presented in Table 1.

Table 1: Recommended Dose Reductions for BRAFTOVI for Adverse Reactions – Melanoma or NSCLC

Action | Recommended Dose
First dose reduction | 300 mg (four 75 mg capsules) orally once daily
Second dose reduction | 225 mg (three 75 mg capsules) orally once daily
Subsequent modification | Permanently discontinue if unable to tolerate BRAFTOVI 225 mg (three 75 mg capsules) once daily

BRAF V600E Mutation-Positive Metastatic Colorectal Cancer (CRC)

When BRAFTOVI is administered in combination with cetuximab and mFOLFOX6 or FOLFIRI

- Continue BRAFTOVI with mFOLFOX6 or FOLFIRI if cetuximab is permanently discontinued.
- Permanently discontinue BRAFTOVI if cetuximab and mFOLFOX6 or FOLFIRI are permanently discontinued.

When BRAFTOVI is administered in combination with cetuximab

- Permanently discontinue BRAFTOVI when cetuximab is permanently discontinued.

Dose reductions for adverse reactions associated with BRAFTOVI are presented in Table 2.

Table 2: Recommended Dose Reductions for BRAFTOVI for Adverse Reactions – CRC
Action | Recommended Dose
First dose reduction | 225 mg (three 75 mg capsules) orally once daily
Second dose reduction | 150 mg (two 75 mg capsules) orally once daily
Subsequent modification | Permanently discontinue if unable to tolerate BRAFTOVI 150 mg (two 75 mg capsules) once daily

BRAF V600E or V600K Mutation-Positive Unresectable or Metastatic Melanoma, BRAF V600E Mutation-Positive Metastatic Colorectal Cancer (CRC), or BRAF V600E Mutation-Positive NSCLC

Dosage modifications for adverse reactions associated with BRAFTOVI are presented in Table 3.

Table 3: Recommended Dosage Modifications for BRAFTOVI for Adverse Reactions
Severity of Adverse Reaction [National Cancer Institute Common Terminology Criteria for Adverse Events (NCI CTCAE) version 4.03.] | Dose Modification for BRAFTOVI
New Primary Malignancies [see Warnings and Precautions (5.1)]
Noncutaneous RAS Mutation-positive Malignancies | Permanently discontinue BRAFTOVI.
Cardiomyopathy [see Warnings and Precautions (5.3)]
- Symptomatic congestive heart failure or absolute decrease in LVEF of greater than 20% from baseline that is also below LLN | Reduce BRAFTOVI by one dose level [see Dosage and Administration (2.3)].; - If LVEF improves to at least institutional LLN and absolute decrease to less than or equal to 10% compared to baseline, continue BRAFTOVI at the reduced dose [see Dosage and Administration (2.3)]. - If no improvement, withhold BRAFTOVI until improves to at least institutional LLN and absolute decrease to less than or equal to 10% compared to baseline and then resume at the reduced dose or reduce dose an additional dose level.
Hepatotoxicity [see Warnings and Precautions (5.4)]
- Grade 2 AST or ALT increased | Maintain BRAFTOVI dose.; - If no improvement within 4 weeks, withhold BRAFTOVI until improves to Grade 0-1 or to pretreatment/baseline levels and then resume at same dose.
- Grade 3 or 4 AST or ALT increased | See Other Adverse Reactions.
Uveitis [see Warnings and Precautions (5.6)]
- Grade 1–3 | If Grade 1 or 2 does not respond to specific ocular therapy, or for Grade 3 uveitis, withhold BRAFTOVI for up to 6 weeks.; - If improved, resume at same or reduced dose. - If not improved, permanently discontinue BRAFTOVI.
- Grade 4 | Permanently discontinue BRAFTOVI.
QTc Prolongation [see Warnings and Precautions (5.7)]
- QTcF greater than 500 ms and less than or equal to 60 ms increase from baseline | Withhold BRAFTOVI until QTcF less than or equal to 500 ms. Resume at reduced dose.; - If more than one recurrence, permanently discontinue BRAFTOVI.
- QTcF greater than 500 ms and greater than 60 ms increase from baseline | Permanently discontinue BRAFTOVI.
Dermatologic [Other than Hand-foot Skin Reaction (HFSR)] [see Adverse Reactions (6.1)]
- Grade 2 | If no improvement within 2 weeks, withhold BRAFTOVI until Grade 0–1. Resume at same dose.
- Grade 3 | Withhold BRAFTOVI until Grade 0–1. Resume at same dose if first occurrence or reduce dose if recurrent.
- Grade 4 | Permanently discontinue BRAFTOVI.
Other Adverse Reactions (including Hemorrhage) [see Warnings and Precautions (5)] and HFSR [see Adverse Reactions (6.1)] [Dose modification of BRAFTOVI when administered with binimetinib or with cetuximab is not recommended for new primary cutaneous malignancies; ocular events other than uveitis, iritis, and iridocyclitis; interstitial lung disease/pneumonitis; creatine phosphokinase (CPK) elevation; rhabdomyolysis; and venous thromboembolism.]
- Recurrent Grade 2 or - First occurrence of any Grade 3 | Withhold BRAFTOVI for up to 4 weeks.; - If improves to Grade 0–1 or to pretreatment/baseline level, resume at reduced dose. - If no improvement, permanently discontinue BRAFTOVI.
- First occurrence of any Grade 4 | Permanently discontinue BRAFTOVI or Withhold BRAFTOVI for up to 4 weeks.; - If improves to Grade 0–1 or to pretreatment/baseline level, then resume at reduced dose. - If no improvement, permanently discontinue BRAFTOVI.
- Recurrent Grade 3 | Consider permanently discontinuing BRAFTOVI.
- Recurrent Grade 4 | Permanently discontinue BRAFTOVI.

Refer to the binimetinib or cetuximab prescribing information for dose modifications for adverse reactions associated with each product, as appropriate.

2.6 Dose Modifications for Coadministration with Strong or Moderate CYP3A4 Inhibitors

Avoid coadministration of BRAFTOVI with strong or moderate CYP3A4 inhibitors. If coadministration is unavoidable, reduce the BRAFTOVI dose according to the recommendations in Table 4. After the inhibitor has been discontinued for 3 to 5 elimination half-lives, resume the BRAFTOVI dose that was taken prior to initiating the CYP3A4 inhibitor [see Drug Interactions (7.1), Clinical Pharmacology (12.3)].

Table 4: Recommended Dose Reductions for BRAFTOVI for Coadministration with Strong or Moderate CYP3A4 Inhibitors
Current Daily Dose [Current daily dose refers to recommended dose of BRAFTOVI based on indication or reductions for adverse reactions based on dosing recommendations in Table 1 (Melanoma) and Table 2 (CRC).] | Dose for Coadministration with Moderate CYP3A4 Inhibitor | Dose for Coadministration with Strong CYP3A4 Inhibitor
450 mg | 225 mg (three 75 mg capsules) | 150 mg (two 75 mg capsules)
300 mg | 150 mg (two 75 mg capsules) | 75 mg
225 mg | 75 mg | 75 mg
150 mg | 75 mg | 75 mg [Encorafenib exposure at the 75 mg QD BRAFTOVI dosage when coadministered with a strong CYP3A4 inhibitor is expected to be higher than at the 150 mg QD dosage in the absence of a CYP3A4 inhibitor and similar to exposure at the 225 mg QD dosage in the absence of a CYP3A4 inhibitor. Monitor patients closely for adverse reactions and use clinical judgment when using BRAFTOVI with strong CYP3A4 inhibitors at the 150 mg dose level.]

3 DOSAGE FORMS AND STRENGTHS

Capsules: 75 mg, hard gelatin, stylized "A" on beige cap and "LGX 75mg" on white body.

4 CONTRAINDICATIONS

None.

5 WARNINGS AND PRECAUTIONS

5.1 New Primary Malignancies

New primary malignancies, cutaneous and noncutaneous, have been observed in patients treated with BRAF inhibitors and can occur with BRAFTOVI.

Cutaneous Malignancies

In COLUMBUS, cutaneous squamous cell carcinoma (cuSCC), including keratoacanthoma (KA), occurred in 2.6%, and basal cell carcinoma occurred in 1.6% of patients who received BRAFTOVI in combination with binimetinib. Median time to first occurrence of cuSCC/KA was 5.8 months (range 1 to 9 months) [see Adverse Reactions (6.1)].

For patients who received BRAFTOVI as a single agent, cuSCC/KA was reported in 8%, basal cell carcinoma in 1%, and a new primary melanoma in 5% of patients.

In BEACON CRC, cuSCC/KA occurred in 1.4% of patients with CRC, and a new primary melanoma occurred in 1.4% of patients who received BRAFTOVI in combination with cetuximab.

In PHAROS, cuSCC and skin papilloma, each occurred in 2% of patients who received BRAFTOVI in combination with binimetinib.

In BREAKWATER, the following cutaneous malignancies occurred in patients receiving BRAFTOVI in combination with cetuximab and mFOLFOX6: melanocytic nevus in 5.6%, skin papilloma in 3%, basal cell carcinoma in 1.3%, squamous cell carcinoma of skin in 0.9%, keratoacanthoma in 0.4% and malignant melanoma in situ in 0.4%. In patients who received BRAFTOVI in combination with cetuximab and FOLFIRI, skin papilloma occurred in 2.8% and keratoacanthoma in 1.4% of patients.

Perform dermatologic evaluations prior to initiating treatment, every 2 months during treatment, and for up to 6 months following discontinuation of treatment. Manage suspicious skin lesions with excision and dermatopathologic evaluation. Dose modification is not recommended for new primary cutaneous malignancies.

Noncutaneous Malignancies

Based on its mechanism of action, BRAFTOVI may promote malignancies associated with activation of RAS through mutation or other mechanisms [see Warnings and Precautions (5.2)]. Monitor patients receiving BRAFTOVI for signs and symptoms of noncutaneous malignancies. Discontinue BRAFTOVI for RAS mutation-positive noncutaneous malignancies [see Dosage and Administration (2.5)].

5.2 Tumor Promotion in BRAF Wild-Type Tumors

In vitro experiments have demonstrated paradoxical activation of MAP-kinase signaling and increased cell proliferation in BRAF wild-type cells, which are exposed to BRAF inhibitors. Confirm evidence of BRAF V600E or V600K mutation prior to initiating BRAFTOVI [see Indications and Usage (1), Dosage and Administration (2.1)].

5.3 Cardiomyopathy

Cardiomyopathy, manifesting as left ventricular dysfunction associated with symptomatic or asymptomatic decreases in ejection fraction, has been reported in patients treated with BRAFTOVI in combination with binimetinib. In COLUMBUS, evidence of cardiomyopathy (decreased in LVEF below the institutional LLN with an absolute decreased in LVEF ≥10% below baseline as detected by echocardiography or MUGA) occurred in 7% of patients receiving BRAFTOVI plus binimetinib. Grade 3 left ventricular dysfunction occurred in 1.6% of patients. The median time to first occurrence of left ventricular dysfunction (any grade) in patients receiving BRAFTOVI in combination with binimetinib was 3.6 months (range 0 to 21 months). Cardiomyopathy resolved in 87% of patients receiving BRAFTOVI plus binimetinib.

In PHAROS, evidence of cardiomyopathy (decrease in LVEF below the institutional LLN with an absolute decrease in LVEF ≥10% below baseline as detected by echocardiography or MUGA) occurred in 11% of patients receiving BRAFTOVI in combination with binimetinib. Grade 3 left ventricular dysfunction occurred in 1% of patients. Cardiomyopathy resolved in 82% of patients receiving BRAFTOVI plus binimetinib.

Assess ejection fraction by echocardiogram or MUGA scan prior to initiating treatment, one month after initiating treatment, and every 2 to 3 months during treatment. The safety of BRAFTOVI in combination with binimetinib has not been established in patients with baseline ejection fraction that is either below 50% or below the institutional lower limit of normal (LLN). Patients with cardiovascular risk factors should be monitored closely when treated with BRAFTOVI.

Withhold, reduce dose, or permanently discontinue based on severity of adverse reaction [see Dosage and Administration (2.3), Adverse Reactions (6.1)].

5.4 Hepatotoxicity

Hepatotoxicity can occur when BRAFTOVI is administered in combination with binimetinib. In COLUMBUS, the incidence of Grade 3 or 4 increases in liver function laboratory tests in patients receiving BRAFTOVI in combination with binimetinib was 6% for alanine aminotransferase (ALT), 2.6% for aspartate aminotransferase (AST), and 0.5% for alkaline phosphatase. In PHAROS, the incidence of Grade 3 or 4 increases in liver function laboratory tests in patients receiving BRAFTOVI in combination with binimetinib was 10% for AST, 9% for ALT, and 3.2% for alkaline phosphatase.

In BREAKWATER, the incidence of Grade 3 or 4 increases in liver function laboratory tests in patients receiving BRAFTOVI in combination with cetuximab and mFOLFOX6 was 2.6% for alkaline phosphatase, and 1.3% each for ALT and AST. In patients receiving BRAFTOVI in combination with cetuximab and FOLFIRI, the incidence of Grade 3 or 4 increases in liver function laboratory tests was 1.5% each for ALT and AST.

Monitor liver laboratory tests before initiation of BRAFTOVI, monthly during treatment, and as clinically indicated. Withhold, reduce dose, or permanently discontinue based on severity of adverse reaction [see Dosage and Administration (2.3), Adverse Reactions (6.1)].

5.5 Hemorrhage

In COLUMBUS, hemorrhage occurred in 19% of patients receiving BRAFTOVI in combination with binimetinib; Grade 3 or greater hemorrhage occurred in 3.2% of patients. The most frequent hemorrhagic events were gastrointestinal, including rectal hemorrhage (4.2%), hematochezia (3.1%), and hemorrhoidal hemorrhage (1%). Fatal intracranial hemorrhage in the setting of new or progressive brain metastases occurred in 1.6% of patients.

In BEACON CRC, hemorrhage occurred in 19% of patients receiving BRAFTOVI in combination with cetuximab; Grade 3 or higher hemorrhage occurred in 1.9% of patients, including fatal gastrointestinal hemorrhage in 0.5% of patients. The most frequent hemorrhagic events were epistaxis (6.9%), hematochezia (2.3%), and rectal hemorrhage (2.3%).

In PHAROS, hemorrhage occurred in 12% of patients receiving BRAFTOVI in combination with binimetinib including fatal hemorrhage intracranial (1%); Grade 3 or 4 hemorrhage occurred in 4.1% of patients. The most frequent hemorrhagic events were anal hemorrhage and hemothorax (2% each).

In BREAKWATER, hemorrhage occurred in 34% of patients receiving BRAFTOVI in combination with cetuximab and mFOLFOX6; Grade 3 or 4 hemorrhage occurred in 3% of patients. In patients receiving BRAFTOVI in combination with cetuximab and FOLFIRI, hemorrhage occurred in 21% of patients.

Withhold, reduce dose, or permanently discontinue based on severity of adverse reaction [see Dosage and Administration (2.5), Adverse Reactions (6.1)].

5.6 Uveitis

Uveitis, including iritis and iridocyclitis, has been reported in patients treated with BRAFTOVI in combination with binimetinib. In COLUMBUS, the incidence of uveitis among patients treated with BRAFTOVI in combination with binimetinib was 4%. In PHAROS, the incidence of uveitis among patients treated with BRAFTOVI in combination with binimetinib was 1%. In BREAKWATER, the incidence of uveitis among patients who received BRAFTOVI in combination with cetuximab and mFOLFOX6 was 0.4%.

Assess for visual symptoms at each visit. Perform an ophthalmologic evaluation at regular intervals and for new or worsening visual disturbances, and to follow new or persistent ophthalmologic findings. Withhold, reduce dose, or permanently discontinue based on severity of adverse reaction [see Dosage and Administration (2.5), Adverse Reactions (6.1)].

5.7 QT Prolongation

BRAFTOVI is associated with dose-dependent QTc interval prolongation in some patients [see Clinical Pharmacology (12.2)]. In COLUMBUS, an increase in QTcF to >500 ms was measured in 0.5% (1/192) of patients who received BRAFTOVI in combination with binimetinib. In PHAROS, an increase in QTcF to >500 ms was measured in 2.1% (2/95) of patients who received BRAFTOVI in combination with binimetinib.

In BREAKWATER, an increase of QTcF >500 ms was measured in 4% (9/226) of patients receiving BRAFTOVI in combination with cetuximab and mFOLFOX6. In patients receiving BRAFTOVI in combination with cetuximab and FOLFIRI, an increase of QTcF >500 ms was measured in 1.5% (1/65) of patients.

Monitor patients who already have or who are at significant risk of developing QTc prolongation, including patients with known long QT syndromes, clinically significant bradyarrhythmias, severe or uncontrolled heart failure and those taking other medicinal products associated with QT prolongation. Correct hypokalemia and hypomagnesemia prior to and during BRAFTOVI administration. Withhold, reduce dose, or permanently discontinue for QTc >500 ms [see Dosage and Administration (2.5), Adverse Reactions (6.1)].

5.8 Embryo-Fetal Toxicity

Based on its mechanism of action, BRAFTOVI can cause fetal harm when administered to a pregnant woman. Encorafenib produced embryo-fetal developmental changes in rats and rabbits and was an abortifacient in rabbits at doses greater than or equal to those resulting in exposures approximately 26 (in the rat) and 178 (in the rabbit) times the human exposure at the recommended dose of 450 mg, with no clear findings at lower doses.

Advise pregnant women and females of reproductive potential of the potential risk to a fetus. Advise females of reproductive potential to use an effective, nonhormonal method of contraception since BRAFTOVI can render hormonal contraceptives ineffective, during treatment and for 2 weeks after the last dose of BRAFTOVI [see Use in Specific Populations (8.1, 8.3)].

5.9 Risks Associated with BRAFTOVI as a Single Agent

BRAFTOVI when used as a single agent is associated with an increased risk of certain adverse reactions compared to when BRAFTOVI is used in combination with binimetinib. In COLUMBUS, Grades 3 or 4 dermatologic reactions occurred in 21% of patients treated with BRAFTOVI single agent compared to 2% of patients treated with BRAFTOVI in combination with binimetinib [see Warnings and Precautions (5.1), Adverse Reactions (6.1)].

If binimetinib is temporarily interrupted or permanently discontinued, reduce the dose of BRAFTOVI as recommended [see Dosage and Administration (2.5)].

5.10 Risks Associated with Combination Treatment

BRAFTOVI is indicated for use as part of a regimen in combination with binimetinib, in combination with cetuximab, in combination with cetuximab and mFOLFOX6 or FOLFIRI. Refer to the prescribing information for binimetinib, cetuximab and individual product components of mFOLFOX6 and FOLFIRI for additional risk information.

6 ADVERSE REACTIONS

The following adverse reactions are described elsewhere in the labeling:

- New Primary Malignancies [see Warnings and Precautions (5.1)]
- Tumor Promotion in BRAF Wild-Type Tumors [see Warnings and Precautions (5.2)]
- Cardiomyopathy [see Warnings and Precautions (5.3)]
- Hepatotoxicity [see Warnings and Precautions (5.4)]
- Hemorrhage [see Warnings and Precautions (5.5)]
- Uveitis [see Warnings and Precautions (5.6)]
- QT Prolongation [see Warnings and Precautions (5.7)]
- Embryo-Fetal Toxicity [see Warnings and Precautions (5.8)]
- Risks Associated with BRAFTOVI as a Single Agent [see Warnings and Precautions (5.9)]
- Risks Associated with Combination Treatment [see Warnings and Precautions (5.10)]

6.1 Clinical Trials Experience

Because clinical trials are conducted under widely varying conditions, adverse reaction rates observed in the clinical trials of a drug cannot be directly compared to rates in the clinical trials of another drug and may not reflect the rates observed in practice.

BRAF V600E or V600K Mutation-Positive Unresectable or Metastatic Melanoma

The safety of BRAFTOVI in combination with binimetinib is described in 192 patients with BRAF V600 mutation-positive unresectable or metastatic melanoma who received BRAFTOVI (450 mg once daily) in combination with binimetinib (45 mg twice daily) in a randomized open-label, active-controlled trial (COLUMBUS).

The COLUMBUS trial [see Clinical Studies (14.1)] excluded patients with a history of Gilbert's syndrome, abnormal left ventricular ejection fraction, prolonged QTc (>480 ms), uncontrolled hypertension, and history or current evidence of retinal vein occlusion. The median duration of exposure was 11.8 months for patients treated with BRAFTOVI in combination with binimetinib and 6.2 months for patients treated with vemurafenib.

The most common (≥25%) adverse reactions in patients receiving BRAFTOVI in combination with binimetinib were fatigue, nausea, vomiting, abdominal pain, and arthralgia.

Adverse reactions leading to dose interruptions of BRAFTOVI occurred in 30% of patients receiving BRAFTOVI in combination with binimetinib; the most common were nausea (7%), vomiting (7%), and pyrexia (4%). Adverse reactions leading to dose reductions of BRAFTOVI occurred in 14% of patients receiving BRAFTOVI in combination with binimetinib; the most common were arthralgia (2%), fatigue (2%), and nausea (2%). Five percent (5%) of patients receiving BRAFTOVI in combination with binimetinib experienced an adverse reaction that resulted in permanent discontinuation of BRAFTOVI; the most common were hemorrhage in 2% and headache in 1% of patients.

Table 5 and Table 6 present adverse drug reactions and laboratory abnormalities, respectively, identified in COLUMBUS. The COLUMBUS trial was not designed to demonstrate a statistically significant difference in adverse reaction rates for BRAFTOVI in combination with binimetinib, as compared to vemurafenib, for any specific adverse reaction listed in Table 5.

Table 5: Adverse Reactions Occurring in ≥10% of Patients Receiving BRAFTOVI in Combination with Binimetinib in COLUMBUS [Grades per National Cancer Institute CTCAE v4.03.]
Adverse Reaction | BRAFTOVI; with binimetinib N=192 |  | Vemurafenib N=186
Adverse Reaction | All Grades (%) | Grades 3 and 4 [Grade 4 adverse reactions limited to fatigue (n=1), pruritus (n=1), and rash (n=1) in the BRAFTOVI with binimetinib arm.] (%) | All Grades (%) | Grades 3 and 4 (%)
General Disorders and Administration Site Conditions
Fatigue [Represents a composite of multiple, related preferred terms.] | 43 | 3 | 46 | 6
Pyrexia | 18 | 4 | 30 | 0
Gastrointestinal Disorders
Nausea | 41 | 2 | 34 | 2
Vomiting | 30 | 2 | 16 | 1
Abdominal pain | 28 | 4 | 16 | 1
Constipation | 22 | 0 | 6 | 1
Musculoskeletal and Connective Tissue Disorders
Arthralgia | 26 | 1 | 46 | 6
Myopathy | 23 | 0 | 22 | 1
Pain in extremity | 11 | 1 | 13 | 1
Skin and Subcutaneous Tissue Disorders
Hyperkeratosis | 23 | 1 | 49 | 1
Rash | 22 | 1 | 53 | 13
Dry skin | 16 | 0 | 26 | 0
Alopecia | 14 | 0 | 38 | 0
Pruritus | 13 | 1 | 21 | 1
Nervous System Disorders
Headache | 22 | 2 | 20 | 1
Dizziness | 15 | 3 | 4 | 0
Peripheral neuropathy | 12 | 1 | 13 | 2
Vascular Disorders
Hemorrhage | 19 | 3 | 9 | 2

BRAFTOVI when used as a single agent increases the risk of certain adverse reactions compared to BRAFTOVI in combination with binimetinib. In patients receiving BRAFTOVI 300 mg orally once daily as a single agent, the following adverse reactions were observed at a higher rate (≥5%) compared to patients receiving BRAFTOVI in combination with binimetinib: palmar-plantar erythrodysesthesia syndrome (51% vs. 7%), hyperkeratosis (57% vs. 23%), dry skin (38% vs. 16%), erythema (16% vs. 7%), rash (41% vs. 22%), alopecia (56% vs. 14%), pruritus (31% vs. 13%), arthralgia (44% vs. 26%), myopathy (33% vs. 23%), back pain (15% vs. 9%), dysgeusia (13% vs. 6%), and acneiform dermatitis (8% vs. 3%).

Other clinically important adverse reactions occurring in <10% of patients who received BRAFTOVI in combination with binimetinib were:

Nervous system disorders: Facial paresis

Gastrointestinal disorders: Pancreatitis

Skin and subcutaneous tissue disorders: Panniculitis, Photosensitivity

Immune system disorders: Drug hypersensitivity

Table 6: Laboratory Abnormalities Occurring in ≥10% (All Grades) of Patients Receiving BRAFTOVI in Combination with Binimetinib in COLUMBUS
Laboratory Abnormality | BRAFTOVI; with binimetinib [Grades per National Cancer Institute CTCAE v4.03.]; N=192 |  | Vemurafenib; N=186
Laboratory Abnormality | All Grades; (%) | Grades 3 and 4; (%) | All Grades; (%) | Grades 3 and 4; (%)
Hematology
Anemia | 36 | 3.6 | 34 | 2.2
Leukopenia | 13 | 0 | 10 | 0.5
Lymphopenia | 13 | 2.1 | 30 | 7
Neutropenia | 13 | 3.1 | 4.8 | 0.5
Chemistry
Increased Creatinine | 93 | 3.6 | 92 | 1.1
Increased Gamma Glutamyl Transferase | 45 | 11 | 34 | 4.8
Increased ALT | 29 | 6 | 27 | 2.2
Increased AST | 27 | 2.6 | 24 | 1.6
Hyperglycemia | 28 | 5 | 20 | 2.7
Increased Alkaline Phosphatase | 21 | 0.5 | 35 | 2.2
Hyponatremia | 18 | 3.6 | 15 | 0.5
Hypermagnesemia | 10 | 1.0 | 26 | 0.5

BRAF V600E Mutation-Positive Metastatic Colorectal Cancer (mCRC) in Combination with Cetuximab and fluorouracil-based chemotherapy

The safety of BRAFTOVI 300 mg once daily in combination with cetuximab (500 mg/m^2 every 2 weeks) and mFOLFOX6 was evaluated in 232 patients with BRAF V600E mutation-positive metastatic CRC in a randomized, open-label, active-controlled trial (BREAKWATER) [see Clinical Studies (14.2)]. In a separate cohort of BREAKWATER (Cohort 3), 139 patients with BRAF V600E mutation-positive mCRC were evaluated; of which 71 patients received BRAFTOVI in combination with cetuximab (500 mg/m^2 every 2 weeks) and FOLFIRI. Patients with pancreatitis, leptomeningeal disease, chronic inflammatory bowel disease requiring medical intervention, as well as clinically significant cardiovascular diseases [e.g., myocardial infarction, acute coronary syndromes, NYHA Class ≥II congestive heart failure, prolonged QTcF interval (≥480 ms), history of prolonged QT syndrome] and active infectious conditions were excluded.

BRAFTOVI in combination with cetuximab and mFOLFOX6

Among patients who received BRAFTOVI, 73% were exposed for 6 months or longer and 48% were exposed for one year or longer.

Serious adverse reactions occurred in 46% of patients who received BRAFTOVI in combination with cetuximab and mFOLFOX6. Serious adverse reactions in >3% of patients included intestinal obstruction (4.7%), pyrexia (3.9%), sepsis (3.4%), and abdominal pain (3.4%).

Fatal intestinal obstruction occurred in 0.9%, and fatal large intestinal perforation and gastrointestinal perforation occurred in 0.4% (each) of patients who received BRAFTOVI in combination with cetuximab and mFOLFOX6.

Permanent discontinuation of BRAFTOVI due to an adverse reaction occurred in 14% of patients. Adverse reactions which resulted in permanent discontinuation of BRAFTOVI in ≥1% of patients included increased lipase and sepsis.

Dosage interruptions of BRAFTOVI due to an adverse reaction occurred in 68% of patients. Adverse reactions which required dosage interruption in ≥5% included neutropenia, anemia, pyrexia, COVID-19, and diarrhea.

Dose reductions of BRAFTOVI due to an adverse reaction occurred in 25% of patients. Adverse reactions leading to dose reductions of BRAFTOVI in ≥2% of patients included fatigue, anemia, arthralgia, increased lipase, nausea, neurotoxicity, and vomiting.

The most common (≥25%) adverse reactions of BRAFTOVI when used in combination with cetuximab and mFOLFOX6 were peripheral neuropathy, nausea, fatigue, diarrhea, decreased appetite, rash, vomiting, hemorrhage, abdominal pain, arthralgia, pyrexia, and constipation.

The most common Grade 3 or 4 laboratory abnormalities (≥10%) of BRAFTOVI when used in combination with cetuximab and mFOLFOX6 were increased lipase, decreased neutrophil count, decreased hemoglobin, decreased white blood cell count, and increased glucose.

Table 7 and Table 8 present adverse drug reactions and laboratory abnormalities, respectively, identified in patients receiving BRAFTOVI in combination with cetuximab and mFOLFOX6 in BREAKWATER.

Table 7: Adverse Reactions Occurring in ≥10% of Patients Receiving BRAFTOVI in Combination with Cetuximab and mFOLFOX6 in BREAKWATER [Grades per National Cancer Institute CTCAE v4.03.]
Adverse Reaction | BRAFTOVI with cetuximab and mFOLFOX6; N=232 |  | mFOLFOX6 with or without bevacizumab or FOLFOXIRI with or without bevacizumab or CAPOX with or without bevacizumab; N=229 |  | mFOLFOX6 with or without bevacizumab; N=115 [Represents a subset of the control arm (mFOLFOX6 with or without bevacizumab or FOLFOXIRI with or without bevacizumab or CAPOX with or without bevacizumab).]
 | All Grades; (%) | Grade 3 or 4; (%) | All Grades; (%) | Grade 3 or 4; (%) | All Grades; (%) | Grade 3 or 4; (%)
Nervous System Disorders
Peripheral neuropathy [Represents multiple related terms.] | 64 | 19 | 53 | 9 | 57 | 10
Headache | 15 | 0.4 | 9 | 0 | 12 | 0
Dysgeusia | 15 | 0 | 14 | 0 | 19 | 0
Neurotoxicity | 11 | 6 | 8 | 0 | 12 | 0
Gastrointestinal Disorders
Nausea | 54 | 3 | 50 | 3.9 | 44 | 2.6
Diarrhea | 42 | 1.3 | 50 | 4.8 | 44 | 2.6
Vomiting | 36 | 3.9 | 22 | 2.2 | 17 | 1.7
Abdominal pain | 32 | 5 | 31 | 1.7 | 30 | 1.7
Constipation | 27 | 0.4 | 23 | 0.4 | 25 | 0.9
Stomatitis | 17 | 2.2 | 16 | 1.3 | 19 | 1.7
General Disorders and Administration Site Conditions
Fatigue | 53 | 7 | 41 | 4.8 | 45 | 7
Pyrexia | 29 | 2.2 | 16 | 0.4 | 17 | 0.9
Metabolism and Nutrition Disorders
Decreased appetite | 38 | 2.2 | 27 | 1.3 | 30 | 2.6
Skin and Subcutaneous Tissue Disorders
Rash | 36 | 1.3 | 6 | 0 | 5 | 0
Alopecia | 23 | 0 | 11 | 0 | 12 | 0
Dry skin | 22 | 0.4 | 6 | 0 | 5 | 0
Dermatitis acneiform | 20 | 0.9 | 1.3 | 0 | 0.9 | 0
Skin hyperpigmentation | 19 | 0 | 3.1 | 0 | 1.7 | 0
Pruritus | 14 | 0 | 3.9 | 0.4 | 5 | 0.9
Vascular Disorders
Hemorrhage | 34 | 2.6 | 21 | 1.3 | 15 | 1.7
Edema | 11 | 0 | 4.4 | 0 | 6 | 0
Musculoskeletal and Connective Tissue Disorders
Arthralgia | 32 | 2.6 | 6 | 0.4 | 7 | 0.9
Myopathy | 19 | 0 | 4.8 | 0.4 | 6 | 0.9
Musculoskeletal pain | 14 | 0.9 | 10 | 1.3 | 13 | 1.7
Infections and Infestations
COVID-19 | 16 | 0.9 | 17 | 0.4 | 16 | 0.9
Respiratory tract infection | 11 | 0.9 | 11 | 0.4 | 9 | 0.9
Psychiatric Disorders
Insomnia | 13 | 0 | 9 | 0 | 5 | 0

Other clinically important adverse reactions occurring in <10% of patients who received BRAFTOVI in combination with cetuximab and mFOLFOX6 were:

Immune system disorders: Drug hypersensitivity

Skin and subcutaneous tissue disorders: Hyperkeratosis

Gastrointestinal disorders: Pancreatitis

Table 8: Laboratory Abnormalities Occurring in ≥20% (All Grades) of Patients Receiving BRAFTOVI in Combination with Cetuximab and mFOLFOX6 in BREAKWATER [Grades per National Cancer Institute CTCAE v4.03.]
Laboratory Abnormality [The denominator used to calculate the rate varied from 220 to 227 based on the number of patients with a baseline and at least one post-treatment value.] | BRAFTOVI; with cetuximab and mFOLFOX6 |  | mFOLFOX6 with or without bevacizumab; or; FOLFOXIRI with or without bevacizumab; or; CAPOX with or without bevacizumab |  | mFOLFOX6 with or without bevacizumab [Represents a subset of the control arm (mFOLFOX6 with or without bevacizumab or FOLFOXIRI with or without bevacizumab or CAPOX with or without bevacizumab).]
Laboratory Abnormality [The denominator used to calculate the rate varied from 220 to 227 based on the number of patients with a baseline and at least one post-treatment value.] | All Grades; (%) | Grade 3 or 4; (%) | All Grades; (%) | Grade 3 or 4; (%) | All Grades; (%) | Grade 3 or 4; (%)
Hematology
Hemoglobin decreased | 68 | 19 | 50 | 6 | 45 | 7
Activated partial thromboplastin time prolonged | 67 | 5 | 43 | 1 | 50 | 2
Neutrophil count decreased | 66 | 37 | 63 | 35 | 62 | 33
White blood cell decreased | 66 | 12 | 59 | 8 | 56 | 6
Platelet count decreased | 65 | 1 | 57 | 3 | 61 | 4
INR increased | 47 | 1 | 23 | 1 | 24 | 2
Chemistry
Lipase increased | 85 | 53 | 57 | 28 | 53 | 23
Creatinine increased | 70 | 1 | 72 | 1 | 75 | 0
Glucose increased | 56 | 11 | 40 | 2 | 39 | 1
Alanine aminotransferase increased | 43 | 1 | 44 | 3 | 46 | 4
Albumin decreased | 42 | 1 | 27 | 1 | 25 | 1
Aspartate aminotransferase increased | 40 | 1 | 41 | 2 | 37 | 3
Alkaline phosphatase increased | 40 | 3 | 35 | 1 | 32 | 3
Potassium decreased | 38 | 5 | 23 | 5 | 17 | 3
Calcium decreased | 33 | 4 | 22 | 2 | 19 | 2
Magnesium decreased | 27 | 1 | 12 | 1 | 9 | 0
Sodium decreased | 23 | 3 | 17 | 4 | 16 | 5

BRAFTOVI in combination with cetuximab and FOLFIRI

Among patients who received BRAFTOVI, 81% were exposed for 6 months or longer and 17% were exposed for one year or longer.

Serious adverse reactions occurred in 39% of patients who received BRAFTOVI in combination with cetuximab and FOLFIRI. Serious adverse reactions in >3% of patients included febrile neutropenia (5.6%) and infusion related reaction (4.2%).

Fatal gastrointestinal perforation occurred in 1.4% of patients who received BRAFTOVI in combination with cetuximab and FOLFIRI.

Permanent discontinuation of BRAFTOVI due to an adverse reaction occurred in 9% of patients. Adverse reactions which resulted in permanent discontinuation of BRAFTOVI in ≥1% of patients included completed suicide, diarrhea, dyspnea, gastrointestinal perforation, infusion related reaction and pyrexia.

Dosage interruptions of BRAFTOVI due to an adverse reaction occurred in 55% of patients. Adverse reactions which required dosage interruption in ≥5% included neutropenia, diarrhea, and febrile neutropenia.

Dose reductions of BRAFTOVI due to an adverse reaction occurred in 20% of patients. Adverse reactions leading to dose reductions of BRAFTOVI in ≥2% of patients included nausea, vomiting, decreased appetite, fatigue, and diarrhea.

The most common (≥25%) adverse reactions of BRAFTOVI when used in combination with cetuximab and FOLFIRI were nausea, diarrhea, fatigue, vomiting, alopecia, constipation, abdominal pain, decreased appetite, and rash.

The most common Grade 3 or 4 laboratory abnormalities (≥10%) of BRAFTOVI when used in combination with cetuximab and FOLFIRI were decreased neutrophil count, increased lipase, decreased white blood cell count, and decreased hemoglobin.

Table 9 and Table 10 present adverse drug reactions and laboratory abnormalities, respectively, identified in patients receiving BRAFTOVI in combination with cetuximab and FOLFIRI in Cohort 3 of BREAKWATER.

Table 9: Adverse Reactions Occurring in ≥10% of Patients Receiving BRAFTOVI in Combination with Cetuximab and FOLFIRI (Cohort 3) in BREAKWATER [Grades per National Cancer Institute CTCAE v4.03.]
Adverse Reaction | BRAFTOVI with cetuximab; and FOLFIRI; N=71 |  | FOLFIRI with or without bevacizumab; N=68
Adverse Reaction | All Grades; (%) | Grade 3 or 4; (%) | All Grades; (%) | Grade 3 or 4; (%)
Gastrointestinal Disorders
Nausea | 61 | 2.8 | 57 | 1.5
Diarrhea [Represents multiple related terms.] | 55 | 10 | 49 | 9
Vomiting | 47 | 2.8 | 31 | 0
Constipation | 31 | 1.4 | 29 | 1.5
Abdominal pain | 30 | 0 | 22 | 1.5
General Disorders and Administration Site Conditions
Fatigue | 47 | 4.2 | 50 | 6
Pyrexia | 17 | 0 | 4.4 | 1.5
Skin and Subcutaneous Tissue Disorders
Alopecia | 35 | 1.4 | 22 | 0
Rash | 27 | 0 | 1.5 | 0
Dry skin | 24 | 0 | 6 | 0
Skin hyperpigmentation | 24 | 0 | 2.9 | 0
Palmar-plantar erythrodysaesthesia syndrome | 17 | 0 | 7 | 0
Dermatitis acneiform | 11 | 0 | 0 | 0
Pruritus | 11 | 0 | 4.4 | 0
Metabolism and Nutrition Disorders
Decreased appetite | 30 | 4.2 | 32 | 2.9
Musculoskeletal and Connective Tissue Disorders
Arthralgia | 24 | 0 | 4.4 | 0
Myopathy | 13 | 0 | 9 | 0
Vascular Disorders
Hemorrhage | 21 | 0 | 22 | 0
Nervous System Disorders
Dysgeusia | 14 | 0 | 4.4 | 0
Headache | 13 | 0 | 13 | 0
Psychiatric Disorders
Insomnia | 13 | 0 | 13 | 0
Neoplasms Benign, Malignant and Unspecified (Including Cysts and Polyps)
Melanocytic nevus | 11 | 0 | 0 | 0
Cardiac Disorders
Arrhythmia | 11 | 0 | 1.5 | 0

Other clinically important adverse reactions occurring in <10% of patients who received BRAFTOVI in combination with cetuximab and FOLFIRI were:

Immune system disorders: Drug hypersensitivity

Skin and subcutaneous tissue disorders: Hyperkeratosis

Gastrointestinal disorders: Pancreatitis

Nervous system disorders: Peripheral neuropathy

Table 10: Laboratory Abnormalities Occurring in ≥20% (All Grades) of Patients Receiving BRAFTOVI in Combination with Cetuximab and FOLFIRI in BREAKWATER [Grades per National Cancer Institute CTCAE v4.03.]
Laboratory Abnormality [The denominator used to calculate the rate varied from 65 to 68 based on the number of patients with a baseline and at least one post‑treatment value.] | BRAFTOVI; with cetuximab and FOLFIRI |  | FOLFIRI with or without bevacizumab
Laboratory Abnormality [The denominator used to calculate the rate varied from 65 to 68 based on the number of patients with a baseline and at least one post‑treatment value.] | All Grades; (%) | Grade 3 or 4; (%) | All Grades; (%) | Grade 3 or 4; (%)
Hematology
White blood cell decreased | 72 | 20 | 67 | 6
Neutrophil count decreased | 69 | 30 | 62 | 32
Hemoglobin decreased | 61 | 10 | 58 | 3
INR increased | 43 | 0 | 21 | 0
Activated partial thromboplastin time prolonged | 33 | 2 | 43 | 0
Platelet count decreased | 21 | 0 | 26 | 0
Chemistry
Creatinine increased | 59 | 2 | 82 | 3
Lipase increased | 46 | 22 | 32 | 12
Glucose increased | 43 | 8 | 35 | 3
Alanine aminotransferase increased | 34 | 2 | 33 | 3
Albumin decreased | 34 | 2 | 26 | 0
Potassium decreased | 34 | 6 | 18 | 6
Calcium decreased | 27 | 2 | 24 | 5
Alkaline phosphatase increased | 22 | 0 | 36 | 5

BRAF V600E Mutation-Positive Metastatic Colorectal Cancer (CRC) in Combination with Cetuximab

The safety of BRAFTOVI 300 mg once daily in combination with cetuximab (400 mg/m^2 initial dose, followed by 250 mg/m^2 weekly) was evaluated in 216 patients with BRAF V600E mutation–positive metastatic CRC in a randomized, open-label, active-controlled trial (BEACON CRC). The BEACON CRC trial [see Clinical Studies (14.3)] excluded patients with a history of Gilbert’s syndrome, abnormal left ventricular ejection fraction, prolonged QTc (>480 ms), uncontrolled hypertension, and history or current evidence of retinal vein occlusion. The median duration of exposure was 4.4 months for patients treated with BRAFTOVI in combination with cetuximab and 1.6 months for patients treated with either irinotecan or infusional 5-fluorouracil (5-FU)/folinic acid (FA)/irinotecan (FOLFIRI) in combination with cetuximab.

The most common (≥25%) adverse reactions in patients receiving BRAFTOVI in combination with cetuximab were fatigue, nausea, diarrhea, dermatitis acneiform, abdominal pain, decreased appetite, arthralgia, and rash.

Adverse reactions leading to dose interruptions of BRAFTOVI occurred in 33% of patients receiving BRAFTOVI in combination with cetuximab; the most common were vomiting (4%), fatigue (4%), nausea (4%), pyrexia (3%), and diarrhea (3%). Adverse reactions leading to dose reductions of BRAFTOVI occurred in 9% of patients receiving BRAFTOVI in combination with cetuximab; the most common were fatigue (2%), arthralgia (2%), and peripheral neuropathy (2%). Ten percent (10%) of patients receiving BRAFTOVI in combination with cetuximab experienced an adverse reaction that resulted in permanent discontinuation of BRAFTOVI. None of the adverse reactions leading to permanent discontinuation of BRAFTOVI occurred in more than one patient (>0.5%).

Table 11 and Table 12 present adverse drug reactions and laboratory abnormalities, respectively, identified in BEACON CRC.

Table 11: Adverse Reactions Occurring in ≥10% of Patients Receiving BRAFTOVI in Combination with Cetuximab in BEACON CRC [Grades per National Cancer Institute CTCAE v4.03.]
Adverse Reaction | BRAFTOVI; with cetuximab; N=216 |  | Irinotecan with cetuximab or FOLFIRI with cetuximab; N=193
Adverse Reaction | All Grades; (%) | ≥Grade 3 [Grade 4-5 adverse reactions in the BRAFTOVI with cetuximab arm were limited to Grade 5 hemorrhage (n=1).]; (%) | All Grades; (%) | ≥Grade 3; (%)
General Disorders and Administration Site Conditions
Fatigue [Represents a composite of multiple, related preferred terms.] | 51 | 7 | 50 | 8
Pyrexia | 17 | 1 | 15 | 1
Gastrointestinal Disorders
Nausea | 34 | 1 | 41 | 1
Diarrhea | 33 | 2 | 48 | 10
Abdominal pain | 30 | 4 | 32 | 5
Vomiting | 21 | 1 | 29 | 3
Constipation | 15 | 0 | 18 | 1
Metabolism and Nutrition Disorders
Decreased appetite | 27 | 1 | 27 | 3
Musculoskeletal and Connective Tissue Disorders
Arthralgia | 27 | 1 | 3 | 0
Myopathy | 15 | 1 | 4 | 0
Pain in extremity | 10 | 0 | 1 | 0
Skin and Subcutaneous Tissue Disorders
Dermatitis acneiform | 32 | 1 | 43 | 3
Rash | 26 | 0 | 26 | 2
Pruritus | 14 | 0 | 6 | 0
Melanocytic nevus | 14 | 0 | 0 | 0
Dry skin | 13 | 0 | 12 | 1
Nervous System Disorders
Headache | 20 | 0 | 3 | 0
Peripheral neuropathy | 12 | 1 | 6 | 0
Vascular Disorders
Hemorrhage | 19 | 2 | 9 | 0
Psychiatric Disorders
Insomnia | 13 | 0 | 6 | 0

Other clinically important adverse reactions occurring in <10% of patients who received BRAFTOVI in combination with cetuximab were:

Gastrointestinal disorders: Pancreatitis

Table 12: Laboratory Abnormalities Occurring in ≥10% (All Grades) of Patients Receiving BRAFTOVI in Combination with Cetuximab in BEACON CRC [Grades per National Cancer Institute CTCAE v4.03.]
Laboratory Abnormality [Based on the number of patients with available baseline and at least one on-treatment laboratory test.] | BRAFTOVI; with cetuximab |  | Irinotecan with cetuximab or FOLFIRI with cetuximab
Laboratory Abnormality [Based on the number of patients with available baseline and at least one on-treatment laboratory test.] | All Grades (%) | Grades 3 and 4 (%) | All Grades (%) | Grades 3 and 4 (%)
Hematology
Anemia | 34 | 4 | 48 | 5
Lymphopenia | 24 | 7 | 35 | 5
Increased activated partial thromboplastin time | 13 | 1 | 7 | 1
Chemistry
Hypomagnesemia | 19 | 0 | 22 | 1
Increased alkaline phosphatase | 18 | 4 | 30 | 7
Increased ALT | 17 | 0 | 29 | 3
Increased AST | 15 | 1 | 22 | 2
Hypokalemia | 12 | 3 | 32 | 5
Hyponatremia | 11 | 2 | 13 | 2

BRAF V600E Mutation-Positive Metastatic Non-Small Cell Lung Cancer (NSCLC)

The safety of BRAFTOVI in combination with binimetinib was evaluated in 98 patients with BRAF V600E mutation-positive metastatic NSCLC who received BRAFTOVI (450 mg once daily) in combination with binimetinib (45 mg twice daily) in an open-label, single-arm trial (PHAROS).

The PHAROS trial [see Clinical Studies (14.3)] excluded patients with abnormal left ventricular ejection fraction, prolonged QTc (>480 ms), uncontrolled hypertension, and history or current evidence of retinal vein occlusion. The median duration of treatment for BRAFTOVI and binimetinib was 9.2 and 8.4 months, respectively.

The most common (≥25%) adverse reactions in patients receiving BRAFTOVI were fatigue, nausea, diarrhea, musculoskeletal pain, vomiting, abdominal pain, visual impairment, constipation, dyspnea, rash, and cough.

Adverse reactions leading to dose interruptions of BRAFTOVI occurred in 59% of patients receiving BRAFTOVI; the most common (≥5%) were diarrhea (17%); nausea (13%); musculoskeletal pain, fatigue (8% each); AST increased (7%); ALT increased, anemia, hemorrhage, vomiting (6% each); and acute kidney injury (5%). Adverse reactions leading to dose reductions of BRAFTOVI occurred in 30% of patients receiving BRAFTOVI; the most common (≥5%) were diarrhea, nausea (8% each); AST increased and fatigue (5% each). A total of 16% of patients receiving BRAFTOVI experienced an adverse reaction that resulted in permanent discontinuation of BRAFTOVI; the most common (≥2%) were diarrhea, musculoskeletal pain (3.1% each); fatigue, rash, nausea, visual impairment, and vomiting (2% each). None of the other adverse reactions leading to permanent discontinuation of BRAFTOVI occurred in more than 1 patient.

Serious adverse reactions occurred in 38% of patients who received BRAFTOVI in combination with binimetinib. Serious adverse reactions occurring in ≥2% of patients were hemorrhage (6%); diarrhea (4.1%); anemia, dyspnea, pneumonia (3.1% each); arrhythmia, device related infection, edema, myocardial infarction, and pleural effusion (2% each). Fatal adverse reactions occurred in 2% of patients who received BRAFTOVI (450 mg once daily) in combination with binimetinib, including intracranial hemorrhage and myocardial infarction (1% each).

Table 13 and Table 14 present adverse drug reactions and laboratory abnormalities, respectively, identified in PHAROS.

Table 13: Adverse Reactions Occurring in ≥10% of Patients Receiving BRAFTOVI in Combination with Binimetinib in PHAROS [Grades per National Cancer Institute CTCAE v4.03.]
Adverse Reaction | BRAFTOVI; with binimetinib N=98
Adverse Reaction | All Grades; (%) | Grades 3 and 4 [One Grade 5 adverse reaction of hemorrhage occurred.]; (%)
General Disorders and Administration Site Conditions
Fatigue [Fatigue includes fatigue, asthenia.] | 61 | 8
Edema [Edema includes edema peripheral, generalized edema, swelling, localized edema, face edema.] | 23 | 1
Pyrexia | 22 | 0
Gastrointestinal Disorders
Nausea | 58 | 3.1
Diarrhea [Diarrhea includes diarrhea, colitis.] | 52 | 7
Vomiting | 37 | 1
Abdominal pain [Abdominal pain includes abdominal pain, abdominal pain upper, abdominal discomfort, epigastric discomfort.] | 32 | 1
Constipation | 27 | 0
Eye Disorders
Visual impairment [Visual impairment includes vision blurred, visual impairment, vitreous floaters, photophobia, visual acuity reduced, photopsia.] | 29 | 2
Musculoskeletal and Connective Tissue Disorders
Musculoskeletal pain [Musculoskeletal pain includes back pain, arthralgia, pain in extremity, myalgia, musculoskeletal chest pain, noncardiac chest pain, neck pain.] | 48 | 4.1
Skin and Subcutaneous Tissue Disorders
Rash [Rash includes rash, rash macular, rash maculo-papular, rash papular, rash pustular, dermatitis acneiform, palmar-plantar erythrodysesthesia syndrome, eczema, skin exfoliation.] | 27 | 3.1
Pruritis [Pruritis includes pruritus, pruritus genital.] | 16 | 0
Dry skin | 13 | 0
Alopecia | 12 | 0
Respiratory, Thoracic and Mediastinal Disorders
Dyspnea [Dyspnea includes dyspnea, dyspnea exertional.] | 27 | 8
Cough [Cough includes cough, productive cough.] | 26 | 0
Nervous System Disorders
Dizziness [Dizziness includes dizziness, balance disorder.] | 17 | 1
Headache | 11 | 0
Metabolism and Nutrition Disorders
Decreased appetite | 14 | 1
Vascular Disorders
Hemorrhage [Hemorrhage includes anal hemorrhage, hemothorax, gastrointestinal hemorrhage, hematochezia, hematuria, hemoptysis, hemorrhage intracranial, hyphema, small intestinal hemorrhage, upper gastrointestinal hemorrhage, vaginal hemorrhage.] | 12 | 4.1
Hypertension | 10 | 5
Cardiac Disorders
Left ventricular dysfunction/cardiomyopathy [Left ventricular dysfunction/cardiomyopathy includes ejection fraction decreased, cardiac failure, cardiac failure congestive.] | 11 | 1
Investigations
Weight increased | 11 | 1
Psychiatric Disorders
Insomnia | 10 | 0

Other clinically important adverse reactions occurring in <10% of patients who received BRAFTOVI in combination with binimetinib were:

Nervous system disorders: Peripheral neuropathy, Dysgeusia, Facial paresis

Gastrointestinal disorders: Pancreatitis

Skin and subcutaneous tissue disorders: Hyperkeratosis, Erythema, Photosensitivity

Immune system disorders: Drug hypersensitivity

Table 14: Laboratory Abnormalities Occurring in ≥10% (All Grades) of Patients Receiving BRAFTOVI with Binimetinib [Grades per National Cancer Institute CTCAE v4.03.]
Laboratory Abnormality [Based on the number of patients with available baseline and at least one on-treatment laboratory test.] | BRAFTOVI with binimetinib
Laboratory Abnormality [Based on the number of patients with available baseline and at least one on-treatment laboratory test.] | All Grades; (%) | Grades 3 and 4; (%)
Hematology
Anemia | 47 | 11
Lymphopenia | 24 | 6
Thrombocytopenia | 20 | 1.1
Leukopenia | 12 | 0
Neutropenia | 12 | 1.1
Chemistry
Increased creatinine | 91 | 3.2
Hyperglycemia | 48 | 6
Increased creatine kinase | 41 | 3.3
Lipase increased | 40 | 14
Increased ALT | 34 | 9
Hypoalbuminemia | 32 | 0
Increased AST | 31 | 10
Increased alkaline phosphatase | 31 | 3.2
Hyperkalemia | 31 | 2.1
Hyponatremia | 26 | 11
Serum amylase increased | 22 | 1.1
Hypocalcemia | 12 | 2.1

7 DRUG INTERACTIONS

7.1 Effect of Other Drugs on BRAFTOVI

Strong or Moderate CYP3A4 Inhibitors

Coadministration of BRAFTOVI with a strong or moderate CYP3A4 inhibitor increases encorafenib plasma concentrations [see Clinical Pharmacology (12.3)] and may increase encorafenib adverse reactions. Avoid coadministration of BRAFTOVI with strong or moderate CYP3A4 inhibitors, including grapefruit juice. If coadministration is unavoidable, reduce the BRAFTOVI dose [see Dosage and Administration (2.6)].

Strong CYP3A4 Inducers

Coadministration of BRAFTOVI with a strong CYP3A4 inducer may decrease encorafenib plasma concentrations [see Clinical Pharmacology (12.3)] and may decrease encorafenib efficacy. Avoid coadministration of BRAFTOVI with strong CYP3A4 inducers.

7.2 Effect of BRAFTOVI on Other Drugs

Sensitive CYP3A4 Substrates

BRAFTOVI is a strong CYP3A4 inducer at steady-state. Concomitant use of BRAFTOVI may decrease the plasma concentrations of CYP3A4 substrates (including hormonal contraceptives), [see Clinical Pharmacology (12.3)], which may reduce the efficacy of these substrates. Avoid the coadministration of BRAFTOVI with CYP3A4 substrates for which a decrease in plasma concentration may lead to reduced efficacy of the substrate. If the coadministration cannot be avoided, see the CYP3A4 substrate product labeling for recommendations.

OATP1B1, OATP1B3, or BCRP Substrates

Coadministration of BRAFTOVI with OATP1B1, OATP1B3, or BCRP substrates can result in increased concentrations of the substrates, and may increase toxicity of these agents. When used in combination, monitor patients closely for signs and symptoms of increased exposure and consider adjusting the dose of these substrates [see Clinical Pharmacology (12.3)].

7.3 Drugs That Prolong the QT Interval

BRAFTOVI is associated with dose-dependent QTc interval prolongation [see Warnings and Precautions (5.7), Clinical Pharmacology (12.2)]. Avoid coadministration of BRAFTOVI with drugs known to prolong the QT/QTc interval.

8 USE IN SPECIFIC POPULATIONS

8.1 Pregnancy

Risk Summary

Based on its mechanism of action, BRAFTOVI can cause fetal harm when administered to a pregnant woman [see Clinical Pharmacology (12.1)]. There are no available clinical data on the use of BRAFTOVI during pregnancy. In animal reproduction studies, encorafenib produced embryo-fetal developmental changes in rats and rabbits and was an abortifacient in rabbits at doses greater than or equal to those resulting in exposures approximately 26 (in the rat) and 178 (in the rabbit) times the human exposure at the clinical dose of 450 mg, with no clear findings at lower doses (see Data). Advise pregnant women and females of reproductive potential of the potential risk to a fetus.

In the U.S. general population, the estimated background risk of major birth defects and miscarriage in clinically recognized pregnancies is 2% to 4% and 15% to 20%, respectively.

Data

Animal Data

In reproductive toxicity studies, administration of encorafenib to rats during the period of organogenesis resulted in maternal toxicity, decreased fetal weights, and increased incidence of total skeletal variations at a dose of 20 mg/kg/day (approximately 26 times the human exposure based on area under the concentration-time curve [AUC] at the recommended clinical dose of 450 mg once daily). In pregnant rabbits, administration of encorafenib during the period of organogenesis resulted in maternal toxicity, decreased fetal body weights, increased incidence of total skeletal variations and increased post-implantation loss, including total loss of pregnancy at a dose of 75 mg/kg/day (approximately 178 times the human exposure based on AUC at the recommended clinical dose of 450 mg once daily). While formal placental transfer studies have not been performed, encorafenib exposure in the fetal plasma of both rats and rabbits was up to 1.7% and 0.8%, respectively, of maternal exposure.

8.2 Lactation

Risk Summary

There are no data on the presence of encorafenib or its metabolites in human milk or the effects of encorafenib on the breastfed child, or the effects on milk production. Because of the potential for serious adverse reactions in a breastfed child from BRAFTOVI, advise women not to breastfeed during treatment with BRAFTOVI and for 2 weeks after the last dose.

8.3 Females and Males of Reproductive Potential

BRAFTOVI can cause fetal harm when administered to a pregnant woman [see Use in Specific Populations (8.1)].

Pregnancy Testing

Verify the pregnancy status of females of reproductive potential prior to initiating BRAFTOVI [see Use in Specific Populations (8.1)].

Contraception

Females

Advise females of reproductive potential to use effective contraception during treatment with BRAFTOVI and for 2 weeks after the last dose. Counsel patients to use a nonhormonal method of contraception since BRAFTOVI has the potential to render hormonal contraceptives ineffective [see Drug Interactions (7.2)].

Infertility

Males

Based on findings in male rats at doses approximately 13 times the human exposure at the 450 mg clinical dose, use of BRAFTOVI may impact fertility in males [see Nonclinical Toxicology (13.1)].

8.4 Pediatric Use

The safety and effectiveness of BRAFTOVI have not been established in pediatric patients.

8.5 Geriatric Use

Of the 690 patients with BRAF mutation-positive melanoma who received BRAFTOVI in combination with binimetinib across multiple clinical trials, 20% were aged 65 to 74 years and 8% were aged 75 years and older [see Clinical Studies (14.1)].

Of the 232 patients with BRAF V600E mutation-positive metastatic CRC who received BRAFTOVI in combination with cetuximab and mFOLFOX6, 84 (36%) were 65 years of age and over and 16 (7%) were 75 years of age and over [see Clinical Studies (14.2)].

Of the 71 patients with BRAF V600E mutation-positive metastatic CRC who received BRAFTOVI in combination with cetuximab and FOLFIRI, 35 (49%) were 65 years of age and over and 9 (13%) were 75 years of age and over [see Clinical Studies (14.2)].

Of the 216 patients with BRAF V600E mutation-positive metastatic CRC who received BRAFTOVI in combination with cetuximab, 62 (29%) were 65 years of age to up to 75 years of age, while 20 (9%) were 75 years of age and over [see Clinical Studies (14.2)].

Of the 98 patients with BRAF V600E mutation-positive metastatic NSCLC who received BRAFTOVI with binimetinib, 62 (63%) were 65 years of age and over and 20 (20%) were 75 years and over [see Clinical Studies (14.3)].

No overall differences in the safety or effectiveness of BRAFTOVI plus binimetinib, BRAFTOVI plus cetuximab, or BRAFTOVI plus cetuximab and mFOLFOX6 or FOLFIRI were observed in older patients as compared to younger patients.

8.6 Hepatic Impairment

No BRAFTOVI dosage adjustment is recommended in patients with mild hepatic impairment (Child-Pugh Class A) [see Clinical Pharmacology (12.3)]. A recommended dosage has not been established in patients with moderate (Child-Pugh Class B) or severe (Child-Pugh Class C) hepatic impairment.

8.7 Renal Impairment

No BRAFTOVI dosage adjustment is recommended in patients with mild to moderate renal impairment (CLcr 30 to <90 mL/min) [see Clinical Pharmacology (12.3)]. A recommended dosage has not been established in patients with severe renal impairment (CLcr <30 mL/min).

10 OVERDOSAGE

Since encorafenib is 86% bound to plasma proteins, hemodialysis is likely to be ineffective in the treatment of overdose with BRAFTOVI.

11 DESCRIPTION

Encorafenib is a kinase inhibitor. The chemical name is methyl N-{(2S)-1-[(4-{3-[5-chloro-2-fluoro-3-(methanesulfonamido)phenyl]-1-(propan-2-yl)-1H-pyrazol-4-yl}pyrimidin-2-yl)amino]propan-2-yl}carbamate. The molecular formula is C22H27ClFN7O4S and the molecular weight is 540 daltons. The chemical structure of encorafenib is shown below:

Encorafenib is a white to almost white powder. In aqueous media, encorafenib is slightly soluble at pH 1, very slightly soluble at pH 2, and insoluble at pH 3 and higher.

BRAFTOVI (encorafenib) capsules for oral use contain 75 mg of encorafenib with the following inactive ingredients: copovidone, poloxamer 188, microcrystalline cellulose, succinic acid, crospovidone, colloidal silicon dioxide, magnesium stearate (vegetable origin). The capsule shell contains gelatin, titanium dioxide, iron oxide red, iron oxide yellow, ferrosoferric oxide, monogramming ink (pharmaceutical glaze, ferrosoferric oxide, propylene glycol).

12 CLINICAL PHARMACOLOGY

12.1 Mechanism of Action

Encorafenib is a kinase inhibitor that targets BRAF V600E, as well as wild-type BRAF and CRAF in in vitro cell-free assays with IC50 values of 0.35, 0.47, and 0.3 nM, respectively. Mutations in the BRAF gene, such as BRAF V600E, can result in constitutively activated BRAF kinases that may stimulate tumor cell growth. Encorafenib was also able to bind to other kinases in vitro including JNK1, JNK2, JNK3, LIMK1, LIMK2, MEK4, and STK36 and reduce ligand binding to these kinases at clinically achievable concentrations (≤0.9 µM).

Encorafenib inhibited in vitro growth of tumor cell lines expressing BRAF V600 E, D, and K mutations. In mice implanted with tumor cells expressing BRAF V600E, encorafenib induced tumor regressions associated with RAF/MEK/ERK pathway suppression.

Encorafenib and binimetinib target two different kinases in the RAS/RAF/MEK/ERK pathway. Compared with either drug alone, coadministration of encorafenib and binimetinib resulted in greater anti-proliferative activity in vitro in BRAF mutation-positive cell lines and greater anti-tumor activity with respect to tumor growth inhibition in BRAF V600E mutant human melanoma xenograft studies in mice. Additionally, the combination of encorafenib and binimetinib delayed the emergence of resistance in BRAF V600E mutant human melanoma xenografts in mice compared to either drug alone. In a BRAF V600E mutant NSCLC patient-derived xenograft model in mice, coadministration of encorafenib and binimetinib resulted in greater anti-tumor activity compared to binimetinib alone, with respect to tumor growth inhibition. Increased tumor growth delay after dosing cessation was also observed with the coadministration compared to either drug alone.

In the setting of BRAF-mutant CRC, induction of EGFR-mediated MAPK pathway activation has been identified as a mechanism of resistance to BRAF inhibitors. Combinations of a BRAF inhibitor and agents targeting EGFR have been shown to overcome this resistance mechanism in nonclinical models. Coadministration of encorafenib and cetuximab had an anti-tumor effect greater than either drug alone, in a mouse model of colorectal cancer with mutated BRAF V600E.

12.2 Pharmacodynamics

Cardiac Electrophysiology

A dedicated study to evaluate the QT prolongation potential of BRAFTOVI has not been conducted. BRAFTOVI is associated with dose-dependent QTc interval prolongation. Based on a central tendency analysis of QTc in a study of adult patients with melanoma who received the recommended dose of BRAFTOVI in combination with binimetinib, the largest mean (90% CI) QTcF change from baseline (ΔQTcF) was 18 (14 to 22) ms [see Warnings and Precautions (5.7)].

12.3 Pharmacokinetics

The pharmacokinetics of encorafenib were studied in healthy subjects and patients with solid tumors, including advanced and unresectable or metastatic cutaneous melanoma harboring a BRAF V600E or V600K mutation, BRAF V600E mutation-positive metastatic CRC. After a single dose, systemic exposure of encorafenib was dose proportional over the dose range of 50 mg to 700 mg (0.1 to 1.6 times the maximum recommended dose of 450 mg). After once-daily dosing, systemic exposure of encorafenib was less than dose proportional over the dose range of 50 mg to 800 mg (0.1 to 1.8 times the maximum recommended dose of 450 mg). Steady-state was reached within 15 days, with exposure being 50% lower compared to Day 1; intersubject variability (CV%) of AUC ranged from 12% to 69%.

Absorption

The median Tmax of encorafenib is 2 hours. At least 86% of the dose is absorbed.

Effect of Food

Following administration of a single dose of BRAFTOVI 100 mg (0.2 times the maximum recommended dose of 450 mg) with a high-fat, high-calorie meal (consisting of approximately 150 calories from protein, 350 calories from carbohydrates, and 500 calories from fat) the mean maximum encorafenib concentration (Cmax) decreased by 36% and there was no effect on AUC.

Distribution

The geometric mean (CV%) of apparent volume of distribution is 164 L (70%). The protein binding of encorafenib is 86% in vitro. The blood-to-plasma concentration ratio is 0.58.

Elimination

The mean (CV%) terminal half-life (t1/2) of encorafenib is 3.5 hours (17%), and the apparent clearance is 14 L/h (54%) at day 1, increasing to 32 L/h (59%) at steady-state at the maximum recommended dose of 450 mg.

Metabolism

Encorafenib is primarily metabolized by CYP3A4 (83%) and to a lesser extent by CYP2C19 (16%) and CYP2D6 (1%).

Excretion

Following a single radiolabeled dose of 100 mg encorafenib, 47% (5% unchanged) of the administered dose was recovered in feces and 47% (2% unchanged) in urine.

Specific Populations

No clinically significant differences in the pharmacokinetics of encorafenib were observed based on age (19 to 94 years), sex, body weight (34 to 168 kg), mild hepatic impairment (Child-Pugh Class A), and mild or moderate renal impairment (CLcr 30 to <90 mL/min). The effect of race or ethnicity, moderate or severe hepatic impairment (Child-Pugh Class B or C), and severe renal impairment (CLcr <30 mL/min) on encorafenib pharmacokinetics have not been studied.

Drug Interaction Studies

Clinical Studies

CYP3A4 Inhibitors: Coadministration of posaconazole (strong CYP3A4 inhibitor) or diltiazem (moderate CYP3A4 inhibitor) increased AUC of encorafenib by 183% and 83%, respectively, and increased Cmax by 68% and 45%, respectively, after a single dose of 50 mg BRAFTOVI (0.1 times the maximum recommended dose of 450 mg).

Strong CYP3A4 Inducers: The effect of a strong CYP3A4 inducer on encorafenib exposure has not been studied [see Drug Interactions (7.1)].

Moderate CYP3A4 Inducers: Repeat dose administration of BRAFTOVI 450 mg once daily and binimetinib 45 mg twice daily with modafinil, a moderate CYP3A4 inducer, decreased encorafenib steady-state AUC by 24% and Cmax by 20%, compared to BRAFTOVI alone.

Effect of encorafenib on CYP3A4 Substrates: Repeat dose administration of BRAFTOVI 450 mg once daily and binimetinib 45 mg twice daily with a single dose of midazolam 2 mg, a sensitive CYP3A4 substrate, decreased midazolam AUC by 82% and Cmax by 74% relative to midazolam 2 mg alone.

Effect of encorafenib on Other CYP Substrates: There was no clinically significant effect of repeat dose administration of BRAFTOVI 450 mg once daily and binimetinib 45 mg twice daily on the exposure of substrates of CYP1A2, CYP2B6, CYP2C9, CYP2C19, and CYP2D6.

Proton Pump Inhibitors: No clinically significant differences in encorafenib pharmacokinetics were observed when coadministered with rabeprazole.

Binimetinib: No clinically significant differences in the pharmacokinetics of binimetinib (UGT1A1 substrate) were observed when coadministered with BRAFTOVI (UGT1A1 inhibitor).

Oxaliplatin: No clinically significant differences in the pharmacokinetics of oxaliplatin were observed when BRAFTOVI 300 mg once daily was coadministered with mFOLFOX6.

Irinotecan: No clinically significant differences in the pharmacokinetics of irinotecan or SN-38 were observed when repeat dose BRAFTOVI 300 mg once daily was coadministered with FOLFIRI.

Transporters: Repeat dose administration of BRAFTOVI 450 mg once daily and binimetinib 45 mg twice daily with a single dose of rosuvastatin (a sensitive substrate for OATP1B1, OATP1B3, and BCRP) increased rosuvastatin Cmax by 168% and AUC by 57%.

In Vitro Studies

CYP/UGT Enzymes: Encorafenib is a reversible inhibitor of UGT1A1.

Transporters: Encorafenib is a substrate of P-glycoprotein (P-gp) but not of breast cancer resistance protein (BCRP), multidrug resistance-associated protein 2 (MRP2), organic anion transporting polypeptide (OATP1B1, OATP1B3) or organic cation transporter (OCT1) at clinically relevant plasma concentrations.

Encorafenib is an inhibitor of P-gp, BCRP, OCT2, organic anion transporter (OAT1, OAT3), OATP1B1, and OATP1B3, but not of OCT1 or MRP2 at clinically relevant plasma concentrations.

13 NONCLINICAL TOXICOLOGY

13.1 Carcinogenesis, Mutagenesis, Impairment of Fertility

Carcinogenicity studies with encorafenib have not been conducted. Encorafenib was not genotoxic in studies evaluating reverse mutations in bacteria, chromosomal aberrations in mammalian cells, or micronuclei in bone marrow of rats.

No dedicated fertility studies were performed with encorafenib in animals. In a general toxicology study in rats, decreased testes and epididymis weights, tubular degeneration in testes, and oligospermia in epididymides were observed at doses approximately 13 times the human exposure at the 450 mg clinical dose based on AUC. No effects on reproductive organs were observed in either sex in any of the nonhuman primate toxicity studies.

13.2 Animal Toxicology and/or Pharmacology

Adverse histopathology findings of hyperplasia and hyperkeratosis occurred in the stomach of rats at encorafenib doses of 20 mg/kg/day (approximately 14 times the human exposure at the 450 mg clinical dose based on AUC) or greater, in both 4 and 13-week studies.

14 CLINICAL STUDIES

14.1 BRAF V600E or V600K Mutation-Positive Unresectable or Metastatic Melanoma

BRAFTOVI in combination with binimetinib was evaluated in a randomized, active-controlled, open-label, multicenter trial (COLUMBUS; NCT01909453). Eligible patients were required to have BRAF V600E or V600K mutation-positive unresectable or metastatic melanoma, as detected using the bioMerieux THxID™ BRAF assay. Patients were permitted to have received immunotherapy in the adjuvant setting and one prior line of immunotherapy for unresectable locally advanced or metastatic disease. Prior use of BRAF inhibitors or MEK inhibitors was prohibited. Randomization was stratified by American Joint Committee on Cancer (AJCC) Stage (IIIB, IIIC, IVM1a or IVM1b, versus IVM1c), Eastern Cooperative Oncology Group (ECOG) performance status (0 versus 1), and prior immunotherapy for unresectable or metastatic disease (yes versus no).

Patients were randomized (1:1:1) to receive BRAFTOVI 450 mg once daily in combination with binimetinib 45 mg twice daily (BRAFTOVI in combination with binimetinib), BRAFTOVI 300 mg once daily, or vemurafenib 960 mg twice daily. Treatment continued until disease progression or unacceptable toxicity. Only the results of the approved dosing (BRAFTOVI 450 mg in combination with binimetinib 45 mg) are described below.

The major efficacy outcome measure was progression-free survival (PFS), as assessed by a blinded independent central review, to compare BRAFTOVI in combination with binimetinib with vemurafenib. Additional efficacy outcome measures included overall survival (OS), as well as objective response rate (ORR) and duration of response (DoR) which were assessed by central review.

A total of 577 patients were randomized, 192 to the BRAFTOVI in combination with binimetinib arm, 194 to the BRAFTOVI arm, and 191 to the vemurafenib arm. Of the 383 patients randomized to either the BRAFTOVI in combination with binimetinib or the vemurafenib arms, the median age was 56 years (20 to 89 years), 59% were male, 91% were White, and 72% had baseline ECOG performance status of 0. Ninety-five percent (95%) had metastatic disease, 65% were Stage IVM1c, and 4% received prior CTLA-4, PD-1, or PD-L1 directed antibodies. Twenty-eight percent (28%) had elevated baseline serum lactate dehydrogenase (LDH), 45% had ≥3 organs with tumor involvement at baseline, and 3% had brain metastases. Based on centralized testing, 100% of patients' tumors tested positive for BRAF mutations; BRAF V600E (88%), BRAF V600K (11%), or both (<1%).

BRAFTOVI in combination with binimetinib demonstrated a statistically significant improvement in PFS compared to vemurafenib. Efficacy results are summarized in Table 15 and Figure 1.

Table 15: Efficacy Results for COLUMBUS
 | BRAFTOVI with binimetinib N=192 | Vemurafenib N=191
Progression-Free Survival
Number of events (%) | 98 (51) | 106 (55)
Progressive disease | 88 (46) | 104 (54)
Death | 10 (5) | 2 (1)
Median PFS, months (95% CI) | 14.9 (11.0, 18.5) | 7.3 (5.6, 8.2)
HR (95% CI) [Estimated with Cox proportional hazard model adjusted by the following stratification factors: American Joint Committee on Cancer (AJCC) Stage (IIIB, IIIC, IVM1a or IVM1b, versus IVM1c) and Eastern Cooperative Oncology Group (ECOG) performance status (0 versus 1).] | 0.54 (0.41, 0.71)
P-value [Log-rank test adjusted by the same stratification factors.] | <0.0001
Overall Survival [Based on a cutoff date of 82.4 months after the date of the PFS analysis.]
Number of events (%) | 139 (72) | 147 (77)
Median OS, months (95% CI) | 33.6 (24.4, 39.2) | 16.9 (14.0, 24.5)
HR (95% CI) | 0.67 (0.53, 0.84)
Overall Response Rate
ORR (95% CI) | 63% (56%, 70%) | 40% (33%, 48%)
CR | 8% | 6%
PR | 55% | 35%
Duration of Response
Median DoR, months (95% CI) | 16.6 (12.2, 20.4) | 12.3 (6.9, 16.9)
CI = Confidence interval; CR = Complete response; DoR = Duration of response; HR = Hazard ratio; NE = Not estimable; ORR = Overall response rate; OS = Overall survival; PFS = Progression-free survival; PR = Partial response.

Figure 1: Kaplan-Meier Curves for Progression-Free Survival in COLUMBUS

14.2 BRAF V600E Mutation-Positive Metastatic Colorectal Cancer (mCRC)

BREAKWATER - BRAFTOVI with Cetuximab and mFOLFOX6

BRAFTOVI in combination with cetuximab and mFOLFOX6 was evaluated in a randomized, active-controlled, open-label, multicenter trial (BREAKWATER CRC; NCT04607421). Eligible patients were required to have BRAF V600E mutation-positive metastatic colorectal cancer (CRC), as detected using the Qiagen therascreen BRAF V600E RGQ polymerase chain reaction (PCR) Kit. Other key eligibility criteria included no prior systemic treatment in the metastatic setting, absence of prior treatment with any selective BRAF inhibitor or EGFR inhibitor, tumor that is not microsatellite instability-high (MSI-H) or mismatch repair deficient (dMMR) unless the patient is ineligible to receive immune checkpoint inhibitors, tumor that is not RAS-mutated or for which RAS mutation status is unknown, and Eastern Cooperative Oncology Group (ECOG) performance status 0-1. Randomization was stratified by ECOG performance status (0 versus 1) and region (US/Canada versus Europe versus Rest of World).

Patients were initially randomized 1:1:1 to one of the following treatment arms, and then 1:1 after discontinuation of enrollment of the BRAFTOVI+cetuximab arm (158 patients):

- BRAFTOVI 300 mg orally once daily in combination with cetuximab 500 mg/m^2 IV infusion every 2 weeks (BRAFTOVI+cetuximab arm)
- BRAFTOVI 300 mg orally once daily in combination with cetuximab 500 mg/m^2 IV infusion every 2 weeks and mFOLFOX6 every 2 weeks (BRAFTOVI+cetuximab+mFOLFOX6 arm)
- mFOLFOX6 (every 2 weeks), or FOLFOXIRI (every 2 weeks), or CAPOX (every 3 weeks), each with or without bevacizumab (administered per prescribing instructions)

mFOLFOX6 consisted of oxaliplatin 85 mg/m^2, leucovorin 400 mg/m^2, 5-FU 400 mg/m^2 IV bolus, then 5-FU 2400 mg/m^2 continuous IV infusion over 46-48 hours; CAPOX consisted of oxaliplatin 130 mg/m^2 IV infusion and capecitabine 1000 mg/m^2 oral tablet twice daily on Days 1-14; FOLFOXIRI consisted of irinotecan 165 mg/m^2, oxaliplatin 85 mg/m^2, leucovorin 400 mg/m^2, 5-FU 2400 or 3200 mg/m^2 (per local standard of care) continuous IV infusion over 46-48 hours.

Treatment continued until disease progression, unacceptable toxicity, withdrawal of consent, lost to follow-up, or death. Only the results of the approved regimen (BRAFTOVI in combination with cetuximab and mFOLFOX6) are described below.

The major efficacy outcome measures were confirmed objective response rate (ORR) and progression‑free survival as assessed by BICR. Additional efficacy outcome measures included overall survival (OS) and duration of response (DoR) as assessed by BICR. PFS and OS were evaluated in all randomized patients. ORR and DoR were evaluated in the first 110 participants randomized in each arm.

A total of 236 patients were randomized to the BRAFTOVI+cetuximab+mFOLFOX6 arm and 243 to the control arm. Of these patients, the median age was 61 years, 49% were female, 59% were White, 37% were Asian, 0.4% were Multiracial, 0.2% were Black or African American, and 2.5% were not reported. Twelve percent (12%) were Hispanic or Latino, 81% were not Hispanic or Latino, and 7% were not reported. Fifty-four percent (54%) had baseline ECOG performance status of 0.

BRAFTOVI in combination with cetuximab and mFOLFOX6 demonstrated statistically significant improvements in ORR, PFS, and OS compared to the active comparator. Efficacy results are summarized in Table 16.

Table 16: Efficacy Results for BRAFTOVI with Cetuximab and mFOLFOX6
Efficacy Parameter | BRAFTOVI; with cetuximab and mFOLFOX6; N=236 | mFOLFOX6 ± bevacizumab; or; FOLFOXIRI ± bevacizumab; or; CAPOX ± bevacizumab; N=243
Progression-Free Survival
Number of events (%) | 122 (52) | 132 (54)
Progressive disease | 105 (45) | 109 (45)
Death | 17 (7) | 23 (9)
Median PFS, months (95% CI) | 12.8 (11.2, 15.9) | 7.1 (6.8, 8.5)
HR (95% CI) [Hazard ratio based on stratified Cox proportional hazards model.] [Stratified by ECOG performance status and geographic region at randomization.] | 0.53 (0.41, 0.68)
P-value [Stratified log-rank test. Tested at 1-sided alpha level of 0.023.] | <0.0001
Objective Response Rate [ORR Subset included the first 110 participants in each arm.]
ORR (95% CI) | 61% (52%, 70%) | 40% (31%, 49%)
CR | 2.7% | 1.8%
PR | 58% | 38%
P-value [Cochran-Mantel-Haenszel test; tested at 1-sided alpha level of 0.001.] | 0.0008
Duration of Response
Median DoR, months (95% CI) | 13.9 (8.5, NE) | 11.1 (6.7, 12.7)
Overall Survival [Interim OS analysis conducted at 81.5% of total events required for final analysis.]
Number of events (%) | 94 (40%) | 148 (61%)
Median OS, months (95% CI) | 30.3 (21.7, NE) | 15.1 (13.7, 17.7)
HR (95% CI) | 0.49 (0.38, 0.63)
P-value [Stratified log-rank test. Tested at 1-sided alpha level of 0.012.] | <0.0001
CI = Confidence interval; CR = Complete response; DoR = Duration of response; N = Number of patients; NE = Not estimable; ORR = Objective response rate; PR = Partial response; HR = Hazard ratio; OS = Overall survival; PFS = Progression-free survival.

Figure 2: Kaplan-Meier Curves for Progression-Free Survival in BREAKWATER (BRAFTOVI plus cetuximab and mFOLFOX6)

Figure 3: Kaplan-Meier Curves for Overall Survival in BREAKWATER (BRAFTOVI plus cetuximab and mFOLFOX6)

BREAKWATER - BRAFTOVI with Cetuximab and FOLFIRI

BRAFTOVI in combination with cetuximab and FOLFIRI (fluorouracil, leucovorin and irinotecan) was evaluated in a separate cohort (Cohort 3) of BREAKWATER CRC (NCT04607421).

Patients were randomized 1:1 to one of the following treatment arms:

- BRAFTOVI 300 mg orally once daily in combination with cetuximab 500 mg/m^2 IV infusion every 2 weeks and FOLFIRI every 2 weeks (BRAFTOVI+cetuximab+FOLFIRI arm)
- FOLFIRI (every 2 weeks) with or without bevacizumab (administered per prescribing instructions)

FOLFIRI consisted of irinotecan 180 mg/m^2 (90 minute IV infusion); leucovorin 400 mg/m^2 (120 minute IV infusion); and 5-FU (400 mg/m^2 IV bolus, then 5-FU 2400 mg/m^2 continuous IV infusion over 46 - 48 hours).

Treatment continued until disease progression, unacceptable toxicity, withdrawal of consent, lost to follow-up, or death.

The major efficacy outcome measure was confirmed objective response rate (ORR) as assessed by BICR. An additional efficacy outcome measure included duration of response (DoR) as assessed by BICR.

A total of 73 patients were randomized to the BRAFTOVI+cetuximab+FOLFIRI arm and 74 to the control arm. Of these patients, the median age was 62 years, 54% were female, 61% were White, 33% were Asian, 1.4% were Native Hawaiian or Other Pacific Islander, 0.7% were Multiracial, and 3.4% were not reported; 10% were Hispanic or Latino, 83% were not Hispanic or Latino, and 7% were not reported. There were no Black or African American patients enrolled in Cohort 3 of BREAKWATER. Sixty percent (60%) had baseline ECOG performance status of 0.

BRAFTOVI in combination with cetuximab and FOLFIRI demonstrated a statistically significant improvement in ORR compared to the active comparator. Efficacy results are summarized in Table 17.

Table 17: Efficacy Results for BRAFTOVI with Cetuximab and FOLFIRI
Efficacy Parameter | BRAFTOVI; with cetuximab and FOLFIRI; N=73 | FOLFIRI with or without bevacizumab; N=74
Objective Response Rate
ORR (95% CI) | 64% (53%, 74%) | 39% (29%, 51%)
CR | 4.1% | 1.4%
PR | 60% | 38%
P-value [Stratified by ECOG performance status at randomization. Cochran-Mantel-Haenszel test; tested at 1-sided alpha level of 0.025.] | 0.0011
Duration of Response
% with DoR ≥6 months | 57% | 35%
CI = Confidence interval; CR = Complete response; DoR = Duration of response; N = Number of patients; ORR = Objective response rate; PR = Partial response.

BEACON CRC-BRAFTOVI with Cetuximab following prior therapy

BRAFTOVI in combination with cetuximab was evaluated in a randomized, active-controlled, open-label, multicenter trial (BEACON CRC; NCT02928224). Eligible patients were required to have BRAF V600E mutation-positive metastatic colorectal cancer (CRC), as detected using the Qiagen therascreen BRAF V600E RGQ polymerase chain reaction (PCR) Kit, with disease progression after 1 or 2 prior regimens. Other key eligibility criteria included absence of prior treatment with a RAF, MEK, or EGFR inhibitor, eligibility to receive cetuximab per local labeling with respect to tumor RAS status, and ECOG performance status (PS) 0-1. Randomization was stratified by Eastern Cooperative Oncology Group (ECOG) performance status (0 versus 1), prior use of irinotecan (yes versus no), and cetuximab product used (US‑licensed versus EU-authorized).

Patients were randomized 1:1:1 to one of the following treatment arms:

- BRAFTOVI 300 mg orally once daily in combination with cetuximab (BRAFTOVI/cetuximab arm)
- BRAFTOVI 300 mg orally once daily in combination with binimetinib and cetuximab
- Irinotecan with cetuximab or FOLFIRI with cetuximab (control arm)

The dosage of cetuximab in all patients was 400 mg/m^2 intravenously for the first dose followed by 250 mg/m^2 weekly.

Patients in the control arm received cetuximab with either irinotecan 180 mg/m^2 intravenously on Days 1 and 15 of each 28‑day cycle or FOLFIRI intravenously (irinotecan 180 mg/m^2 on Days 1 and 15; folinic acid 400 mg/m^2 on Days 1 and 15; then 5-FU 400 mg/m^2 bolus on Days 1 and 15 followed by 5-FU 2400 mg/m^2/day by continuous infusion over 2 days).

Treatment continued until disease progression or unacceptable toxicity. Only the results of the approved regimen (BRAFTOVI in combination with cetuximab) are described below.

The major efficacy outcome measure was overall survival (OS). Additional efficacy outcome measures included progression-free survival (PFS), overall response rate (ORR), and duration of response (DoR) as assessed by blinded independent central review (BICR). OS and PFS were assessed in all randomized patients. ORR and DoR were assessed in the subset of the first 220 patients included in the randomized portion of the BRAFTOVI/cetuximab and control arm of the study.

A total of 220 patients were randomized to the BRAFTOVI/cetuximab arm and 221 to the control arm. Of these 441 patients, the median age was 61 years; 53% were female; 80% were White, 15% were Asian, and 5% were other or not reported. Four percent (4%) were Hispanic or Latino, 90% were not Hispanic or Latino, and 6% were not reported or unknown. Fifty percent (50%) had baseline ECOG performance status of 0; 66% received 1 prior therapy and 34% received 2; 93% received prior oxaliplatin and 52% received prior irinotecan.

BRAFTOVI in combination with cetuximab demonstrated a statistically significant improvement in OS, ORR, and PFS compared to the active comparator. Efficacy results are summarized in Table 18 and Figure 4

Table 18: Efficacy Results from BEACON CRC
 | BRAFTOVI with cetuximab; N=220 | Irinotecan with cetuximab or FOLFIRI with cetuximab; N=221
Overall Survival
Number of Events (%) | 93 (42) | 114 (52)
Median OS, months (95% CI) | 8.4 (7.5, 11.0) | 5.4 (4.8, 6.6)
HR (95% CI) [Stratified by ECOG PS, source of cetuximab (US-licensed versus EU-authorized) and prior irinotecan use at randomization.] [Stratified Cox proportional hazard model.] | 0.60 (0.45, 0.79)
P-value [Stratified log-rank test, tested at alpha level of 0.0084.] | 0.0003
Overall Response Rate (per BICR)
ORR (95% CI) [BRAFTOVI/cetuximab arm (n=113) and control arm (n=107).] | 20% (13%, 29%) | 2% (0%, 7%)
CR | 5% | 0%
PR | 15% | 2%
P-value [Cochran-Mantel-Haenszel test; tested at alpha level of 0.05.] | <0.0001
Median DoR, months (95% CI) | 6.1 (4.1, 8.3) | NR (2.6, NR)
Progression‑Free Survival (per BICR)
Number of events (%) | 133 (60) | 128 (58)
Progressive disease | 110 (50) | 101 (46)
Death | 23 (10) | 27 (12)
Median PFS, months (95% CI) | 4.2 (3.7, 5.4) | 1.5 (1.4, 1.7)
HR (95% CI) | 0.40 (0.31, 0.52)
P-value [Stratified log-rank test, tested at alpha level of 0.0234.] | <0.0001
CI = Confidence interval; CR = Complete response; DoR = Duration of response; HR = Hazard ratio; NR = Not reached; ORR = Overall response rate; OS = Overall survival; PFS = Progression-free survival; PR = Partial response.

Figure 4: Kaplan-Meier Curves for Overall Survival in BEACON CRC

14.3 BRAF V600E Mutation-Positive Metastatic Non-Small Cell Lung Cancer

BRAFTOVI in combination with binimetinib was evaluated in an open-label, multicenter, single-arm study in patients with BRAF V600E mutation-positive metastatic non-small cell lung cancer (NSCLC) (PHAROS; NCT03915951). Eligible patients had a diagnosis of histologically-confirmed metastatic NSCLC with BRAF V600E mutation that was treatment-naïve or had been previously treated with 1 prior line of systemic therapy in the metastatic setting (platinum-based chemotherapy and/or anti-PD-1/PD-L1 therapies), age 18 years or older, Eastern Cooperative Oncology Group (ECOG) performance status (PS) of 0 or 1, and measurable disease as defined by Response Evaluation Criteria in Solid Tumors (RECIST) v1.1. Prior use of BRAF inhibitors or MEK inhibitors was not allowed.

Patients received BRAFTOVI 450 mg once daily and binimetinib 45 mg orally twice daily until disease progression or unacceptable toxicity. The major efficacy outcome measures were objective response rate (ORR) per RECIST v1.1 and duration of response (DoR) as assessed by independent review committee (IRC).

In the efficacy population, BRAF V600E mutation status was determined by prospective local testing using tumor tissue (78%) or blood (22%) specimens. Of the 98 patients with BRAF V600E mutation, 6 patients were enrolled into the trial based on testing of their tumor tissue specimens with the FoundationOne CDx tissue test. Of the remaining 92 patients enrolled based on local testing, 68 patients had their tumor tissue specimens retrospectively confirmed as having BRAF V600E positive status by the FoundationOne CDx tissue test. The remaining patients had either BRAF V600E negative status (n=5) or had unevaluable results (n=19) by the FoundationOne CDx tissue test. In addition, plasma samples from 81 out of 98 patients were retrospectively tested using the FoundationOne Liquid CDx assay. Of the 81 patients, 48 were confirmed positive for BRAF V600E, while 33 patients were BRAF V600E mutation negative by FoundationOne Liquid CDx assay. The remaining 17 samples had unevaluable results with FoundationOne Liquid CDx assay.

The efficacy population included 59 treatment-naïve patients and 39 previously-treated patients. Among these 98 patients, the median age was 70 years (range: 47 to 86); 53% female; 88% White, 7% Asian, 3% Black or African American, and 1% American Indian or Alaska Native; 99% were not Hispanic or Latino; 13% were current smokers and 57% were former smokers; 73% had ECOG PS of 1; and 97% had adenocarcinoma. All patients had metastatic disease, and 8% had brain metastases at baseline.

Efficacy results for patients with BRAF V600E mutation-positive metastatic NSCLC are summarized in Table 19.

Table 19: Efficacy Results for PHAROS
 | BRAFTOVI with binimetinib
Efficacy Parameter | Treatment‑naïve; (N=59) | Previously‑treated; (N=39)
Objective Response Rate [Assessed by Independent Central Review (ICR).]
ORR (95% CI) | 75% (62, 85) | 46% (30, 63)
CR | 15% | 10%
PR | 59% | 36%
Duration of Response [Based on observed duration of response.] | N=44 | N=18
Range in months | 1.4, 51.6+ | 3.8, 45.8+
% with DoR ≥12 months | 64% | 44%
% with DoR ≥24 months | 43% | 22%
CI = Confidence interval; CR = Complete response; DoR = Duration of response; N = Number of patients; NE = Not estimable; ORR = Objective response rate; PR = Partial response.

16 HOW SUPPLIED/STORAGE AND HANDLING

BRAFTOVI (encorafenib) is supplied as 75 mg hard gelatin capsules.

75 mg: stylized "A" on beige cap and "LGX 75mg" on white body, available in cartons (NDC 70255-025-01) containing two bottles of 90 capsules each (NDC 70255-025-02) and cartons (NDC 70255-025-03) containing two bottles of 60 capsules each (NDC 70255-025-04).

STORAGE AND HANDLING

Store at 20°C to 25°C (68°F to 77°F); excursions permitted between 15°C and 30°C (59°F and 86°F) [see USP Controlled Room Temperature]. Do not use if safety seal under cap is broken or missing. Dispense in original bottle. Do not remove desiccant. Protect from moisture. Keep container tightly closed.

17 PATIENT COUNSELING INFORMATION

Advise the patient to read the FDA-authorized patient labeling (Medication Guide).

Inform patients of the following:

New Primary Malignancies

Advise patients that BRAFTOVI increases the risk of developing new primary cutaneous and noncutaneous malignancies. Advise patients to contact their healthcare provider immediately for change in or development of new skin lesions [see Warnings and Precautions (5.1)].

Tumor Promotion in BRAF Wild-Type Tumors

Advise patients of the need to confirm BRAF V600E or V600K mutation prior to initiating BRAFTOVI [see Warnings and Precautions (5.2)].

Cardiomyopathy

Advise patients to report any symptoms of heart failure to their healthcare provider [see Warnings and Precautions (5.3)].

Hepatotoxicity

Advise patients that serial testing of serum liver tests (ALT, AST, bilirubin) is recommended during treatment with BRAFTOVI. Instruct patients to report symptoms of liver dysfunction including jaundice, dark urine, nausea, vomiting, loss of appetite, fatigue, bruising, or bleeding [see Warnings and Precautions (5.4)].

Hemorrhage

Advise patients to notify their healthcare provider immediately with any symptoms suggestive of hemorrhage, such as unusual bleeding [see Warnings and Precautions (5.5)].

Uveitis

Advise patients to contact their healthcare provider if they experience any changes in their vision [see Warnings and Precautions (5.6)].

QT Prolongation

Advise patients that BRAFTOVI can cause QTc interval prolongation and to inform their physician if they have any QTc interval prolongation symptoms, such as syncope [see Warnings and Precautions (5.7)].

Embryo-Fetal Toxicity

- Advise females with reproductive potential of the potential risk to a fetus. Advise females to contact their healthcare provider if they become pregnant, or if pregnancy is suspected, during treatment with BRAFTOVI [see Warnings and Precautions (5.8), Use in Specific Populations (8.1)].
- Advise females of reproductive potential to use effective nonhormonal contraception during treatment with BRAFTOVI and for 2 weeks after the last dose [see Use in Specific Populations (8.3)].

Lactation

Advise women not to breastfeed during treatment with BRAFTOVI and for 2 weeks after the last dose [see Use in Specific Populations (8.2)].

Infertility

Advise males of reproductive potential that BRAFTOVI may impair fertility [see Use in Specific Populations (8.3)].

Drug Interactions

Coadministration of BRAFTOVI with a strong or moderate CYP3A inhibitor may increase encorafenib concentrations; coadministration of BRAFTOVI with a strong CYP3A inducer may decrease encorafenib concentrations. Advise patients that they may need to avoid certain medications while taking BRAFTOVI and to inform their healthcare provider of all concomitant medications, including prescription medicines, over-the-counter drugs, vitamins, and herbal products. Advise patients to avoid grapefruit and grapefruit juice while taking BRAFTOVI [see Drug Interactions (7.1)].

Storage

BRAFTOVI is moisture sensitive. Advise patients to store BRAFTOVI in the original bottle with desiccant and to keep the cap of the bottle tightly closed. Do not remove the desiccants from the bottle.

This product's labeling may have been updated. For the most recent prescribing information, please visit www.pfizer.com.

For medical information about BRAFTOVI, please visit www.pfizermedinfo.com or call 1-800-438-1985.

Distributed by:

Array BioPharma Inc., a wholly owned subsidiary of Pfizer Inc.
3200 Walnut Street
Boulder, CO 80301

© 2024 Array BioPharma Inc. All rights reserved.
BRAFTOVI® is a registered trademark of Array BioPharma Inc. in the United States and various other countries.

LAB-1428-7.0

MEDICATION GUIDE
BRAFTOVI® (braf-TOE-vee)
(encorafenib)
capsules

Important information: BRAFTOVI is used in combination with other medicines, including binimetinib, cetuximab, or cetuximab and fluorouracil-based chemotherapy. Read the Medication Guide that comes with binimetinib if BRAFTOVI is used with binimetinib. Talk to your healthcare provider about cetuximab, or cetuximab and mFOLFOX6 or FOLFIRI if used with BRAFTOVI.

What is the most important information I should know about BRAFTOVI?
BRAFTOVI can cause serious side effects, including:

Risk of new skin cancers. BRAFTOVI can cause skin cancers called cutaneous squamous cell carcinoma or basal cell carcinoma.
Talk to your healthcare provider about your risk for these cancers.
Check your skin and tell your healthcare provider right away about any skin changes, including a:

- new wart
- skin sore or reddish bump that bleeds or does not heal
- change in size or color of a mole

Your healthcare provider should check your skin before treatment with BRAFTOVI, every 2 months during treatment, and for up to 6 months after you stop treatment with BRAFTOVI to look for any new skin cancers.

Your healthcare provider should also check for cancers that may not occur on the skin. Tell your healthcare provider about any new symptoms that develop during treatment with BRAFTOVI.

See "What are the possible side effects of BRAFTOVI?" for more information about side effects.

What is BRAFTOVI?
BRAFTOVI is a prescription medicine used:

- in combination with a medicine called binimetinib to treat people with a type of skin cancer called melanoma:
  - that has spread to other parts of the body or cannot be removed by surgery, and
  - that has a certain type of abnormal "BRAF" gene
- in combination with medicines called cetuximab and mFOLFOX6 (fluorouracil, leucovorin and oxaliplatin) or cetuximab and FOLFIRI (fluorouracil, leucovorin, and irinotecan) to treat adults with cancer of the colon or rectum (colorectal cancer):
  - that has spread to other parts of the body, and
  - that has a certain type of abnormal "BRAF" gene
- in combination with a medicine called cetuximab to treat adults with cancer of the colon or rectum (colorectal cancer) after past treatment:
  - that has spread to other parts of the body, and
  - that has a certain type of abnormal "BRAF" gene
- in combination with a medicine called binimetinib to treat adults with a type of lung cancer called non‑small‑cell lung cancer (NSCLC):
  - that has spread to other parts of the body, and
  - that has a certain type of abnormal "BRAF" gene

BRAFTOVI should not be used to treat people with wild-type‑BRAF melanoma, wild-type‑BRAF colorectal cancer, or wild-type‑BRAF NSCLC.

Your healthcare provider will perform a test to make sure that BRAFTOVI is right for you.
It is not known if BRAFTOVI is safe and effective in children.

Before taking BRAFTOVI, tell your healthcare provider about all of your medical conditions, including if you:

- have had bleeding problems
- have eye problems
- have heart problems, including a condition called long QT syndrome
- have been told that you have low blood levels of potassium, calcium, or magnesium
- have liver or kidney problems
- are pregnant or plan to become pregnant. BRAFTOVI can harm your unborn baby.
  Females who are able to become pregnant:
  - Use effective nonhormonal birth control (contraception) during treatment with BRAFTOVI and for 2 weeks after the last dose of BRAFTOVI. Birth control methods that contain hormones (such as birth control pills, injections or transdermal systems) may not work as well during treatment with BRAFTOVI.
  - Talk to your healthcare provider about birth control methods that may be right for you during this time.
  - Your healthcare provider will do a pregnancy test before you start taking BRAFTOVI. Tell your healthcare provider right away if you become pregnant or think you might be pregnant during treatment with BRAFTOVI.
- are breastfeeding or plan to breastfeed. It is not known if BRAFTOVI passes into your breast milk. Do not breastfeed during treatment with BRAFTOVI and for 2 weeks after the last dose of BRAFTOVI. Talk to your healthcare provider about the best way to feed your baby during this time.

Tell your healthcare provider about all the medicines you take, including prescription and over-the-counter medicines, vitamins, and herbal supplements.
BRAFTOVI and certain other medicines can affect each other, causing side effects or affecting how BRAFTOVI or the other medicines work.
Know the medicines you take. Keep a list of them to show your healthcare provider and pharmacist when you get a new medicine.

How should I take BRAFTOVI?

- Take BRAFTOVI exactly as your healthcare provider tells you. Do not change your dose or stop taking BRAFTOVI unless your healthcare provider tells you to.
- Take BRAFTOVI by mouth 1 time each day.
- BRAFTOVI may be taken with or without food.
- Avoid grapefruit and grapefruit juice during treatment with BRAFTOVI. Grapefruit products may increase the amount of BRAFTOVI in your body.
- If you miss a dose of BRAFTOVI, take it as soon as you remember. If it is within 12 hours of your next scheduled dose, take your next dose at your regular time. Do not make up for the missed dose.
- Do not take an extra dose if you vomit after taking your scheduled dose. Take your next dose at your regular time.
- If you stop treatment with binimetinib or cetuximab, talk to your healthcare provider about your BRAFTOVI treatment. Your BRAFTOVI dose may need to be changed or stopped.

What are the possible side effects of BRAFTOVI?
BRAFTOVI can cause serious side effects, including:

- See "What is the most important information I should know about BRAFTOVI?"
- Heart problems, including heart failure. BRAFTOVI can cause heart problems. Your healthcare provider will check your heart function before and during treatment with BRAFTOVI. Tell your healthcare provider right away if you get any of the following signs and symptoms of a heart problem:
  - feeling like your heart is pounding or racing
  - shortness of breath
  - swelling in your hands, ankles legs or feet
  - feeling faint or lightheaded
- Liver problems. BRAFTOVI can cause liver problems. Your healthcare provider will perform blood tests to check your liver function before and during treatment with BRAFTOVI. Tell your healthcare provider if you get any of the following signs and symptoms of a liver problem:

- yellowing of your skin or your eyes
- dark or brown (tea-colored) urine
- nausea or vomiting
- loss of appetite

- tiredness
- bruising
- bleeding

- Bleeding problems. BRAFTOVI can cause serious bleeding problems, including in your stomach or brain, that can lead to death. Tell your healthcare provider and get medical help right away if you develop any signs of bleeding, including:
  - headaches, dizziness, or feeling weak
  - cough up blood or blood clots
  - vomit blood or your vomit looks like “coffee grounds”
  - red or black stools that look like tar
  - nose bleeds
- Eye problems. BRAFTOVI can cause eye problems. Your healthcare provider should perform an eye exam regularly. Tell your healthcare provider right away if you develop any new or worsening symptoms of eye problems, including:
  - blurred vision, loss of vision, or other vision changes
  - see colored dots
  - see halos (blurred outline around objects)
  - eye pain, swelling, or redness
- Changes in the electrical activity of your heart called QT prolongation. QT prolongation can cause irregular heartbeats that can be life threatening. Your healthcare provider should do tests before you start treatment with BRAFTOVI during your treatment to check your body salts (electrolytes). Tell your healthcare provider right away if you feel faint, lightheaded, dizzy or if you feel your heart beating irregularly or fast during treatment with BRAFTOVI. These symptoms may be related to QT prolongation.

Your healthcare provider may change your dose, temporarily stop, or permanently stop treatment with BRAFTOVI if you have certain side effects.

The most common side effects of BRAFTOVI when taken in combination with binimetinib for melanoma include:

- fatigue
- nausea
- vomiting
- abdominal pain
- pain or swelling of your joints (arthralgia)

The most common side effects of BRAFTOVI when taken in combination with cetuximab and mFOLFOX6 for colorectal cancer include:

- numbness, tingling or burning in your hands or feet (peripheral neuropathy)
- nausea
- fatigue
- diarrhea
- decreased appetite
- rash

- vomiting
- bleeding (hemorrhage)
- stomach-area (abdominal) pain
- pain or swelling of your joints (arthralgia)
- fever
- constipation

The most common side effects of BRAFTOVI when taken in combination with cetuximab and FOLFIRI for colorectal cancer include:

- nausea
- diarrhea
- fatigue
- vomiting
- hair loss (alopecia)

- constipation
- stomach-area (abdominal) pain
- decreased appetite
- rash

The most common side effects of BRAFTOVI when taken in combination with cetuximab for colorectal cancer include:

- fatigue
- nausea
- diarrhea
- acne-like rash (dermatitis acneiform)

- stomach-area (abdominal) pain
- decreased appetite
- pain or swelling of your joints (arthralgia)
- rash

The most common side effects of BRAFTOVI when taken in combination with binimetinib for NSCLC include:

- fatigue
- nausea
- diarrhea
- muscle or joint pain
- vomiting
- stomach-area (abdominal) pain

- blurred vision, loss of vision, or other vision changes
- constipation
- shortness of breath
- rash
- cough

BRAFTOVI may cause fertility problems in males. This may affect your ability to father a child. Talk to your healthcare provider if this is a concern for you.

These are not all of the possible side effects of BRAFTOVI.

Call your doctor for medical advice about side effects. You may report side effects to FDA at 1-800-FDA-1088.

You may also report side effects to Pfizer Inc. at 1-800-438-1985.

How should I store BRAFTOVI?

- Store BRAFTOVI at room temperature between 68°F to 77°F (20°C to 25°C).
- Store BRAFTOVI in the original bottle.
- Keep the BRAFTOVI bottle tightly closed and protect it from moisture.
- BRAFTOVI comes with a desiccant packet in the bottle to help protect your medicine from moisture. Do not remove the desiccant packet from the bottle.

Keep BRAFTOVI and all medicines out of the reach of children.

General information about the safe and effective use of BRAFTOVI.
Medicines are sometimes prescribed for purposes other than those listed in a Medication Guide. Do not use BRAFTOVI for a condition for which it was not prescribed. Do not give BRAFTOVI to other people, even if they have the same symptoms that you have. It may harm them. You can ask your healthcare provider or pharmacist for information about BRAFTOVI that is written for health professionals.

What are the ingredients in BRAFTOVI?
Active ingredient: encorafenib
Inactive ingredients: copovidone, poloxamer 188, microcrystalline cellulose, succinic acid, crospovidone, colloidal silicon dioxide, and magnesium stearate of vegetable origin
Capsule shell: gelatin, titanium dioxide, iron oxide red, iron oxide yellow, ferrosoferric oxide, monogramming ink (pharmaceutical glaze, ferrosoferric oxide, propylene glycol)
Distributed by: Array BioPharma Inc., a wholly owned subsidiary of Pfizer Inc. Boulder, Colorado 80301.
BRAFTOVI® is a registered trademark of Array BioPharma Inc. in the United States and various other countries.
LAB-1429-5.0
For more information, go to www.braftovi.com or call 1-844-792-7729.
© 2024 Array BioPharma Inc. All rights reserved.

This Medication Guide has been approved by the U.S. Food and Drug Administration. Revised: 02/2026

PRINCIPAL DISPLAY PANEL - 75 mg Capsule Bottle Label - 025-02

DISPENSE THE ENCLOSED MEDICATION GUIDE TO EACH PATIENT

NDC 70255-025-02

BRAFTOVI®
(encorafenib) capsules

75 mg

Rx only
90 Capsules

PRINCIPAL DISPLAY PANEL - 75 mg Capsule Bottle Carton

DISPENSE THE ENCLOSED MEDICATION GUIDE TO EACH PATIENT

NDC 70255-025-01

BRAFTOVI®
(encorafenib) capsules

75 mg

Rx only
2 Bottles x 90 Capsules

PRINCIPAL DISPLAY PANEL - 75 mg Capsule Bottle Label - 025-06

DISPENSE THE ENCLOSED MEDICATION GUIDE TO EACH PATIENT

NDC 70255-025-06

BRAFTOVI®
(encorafenib) capsules

75 mg

Rx only
60 Capsules

Sample–
Not For Sale

PRINCIPAL DISPLAY PANEL - 75 mg Capsule Bottle Label - 025-05

DISPENSE THE ENCLOSED MEDICATION GUIDE TO EACH PATIENT

NDC 70255-025-05

BRAFTOVI®
(encorafenib) capsules

75 mg

Rx only
90 Capsules

Sample–
Not For Sale